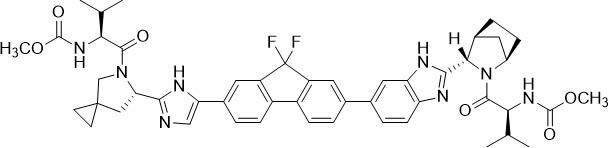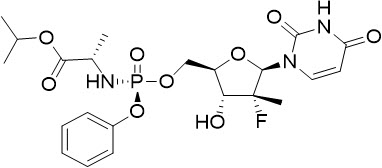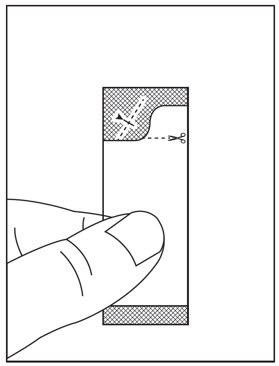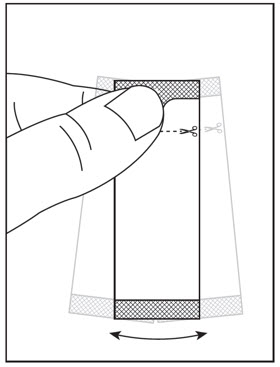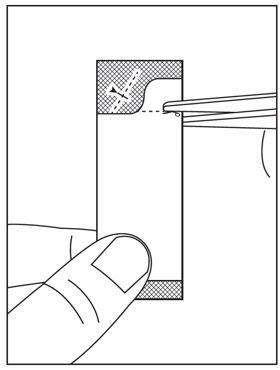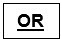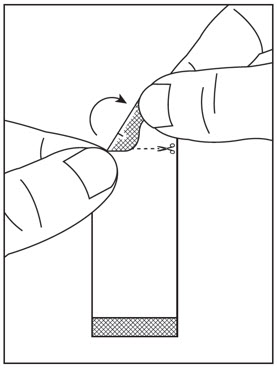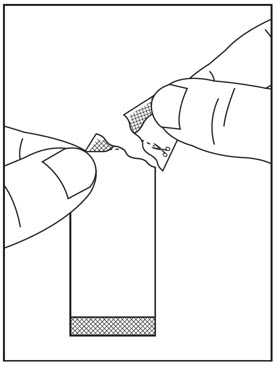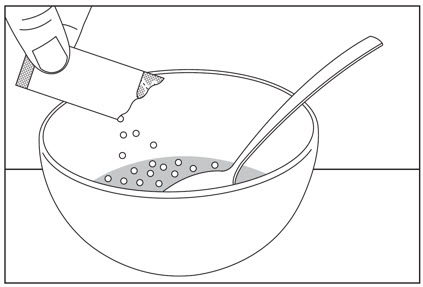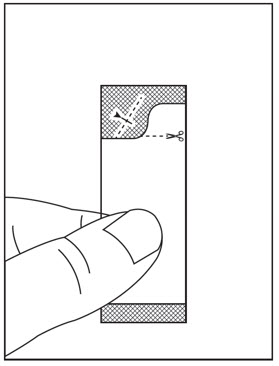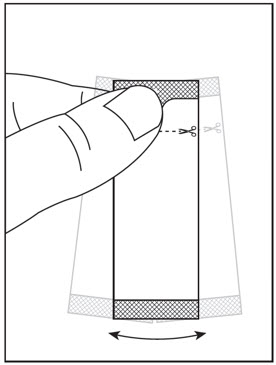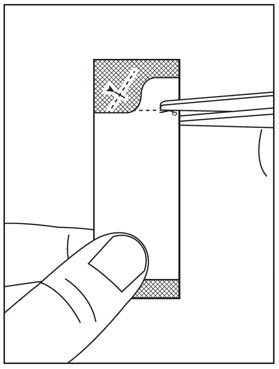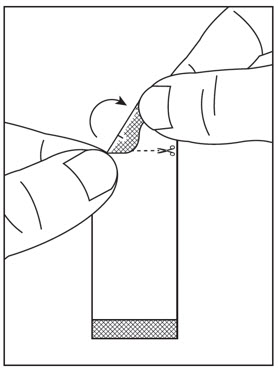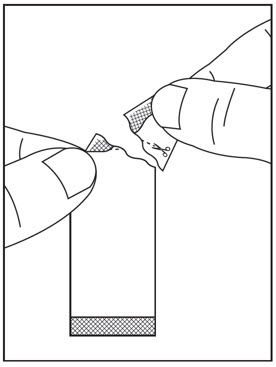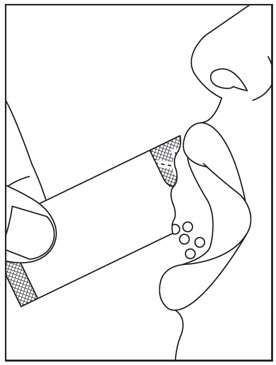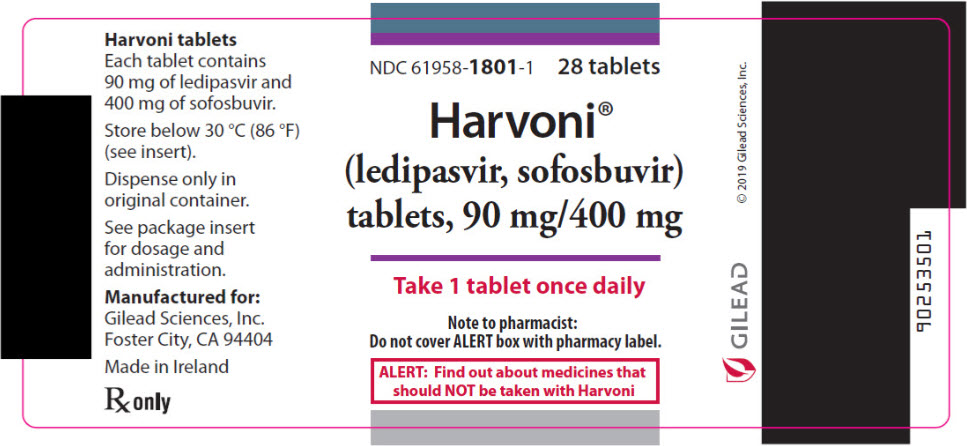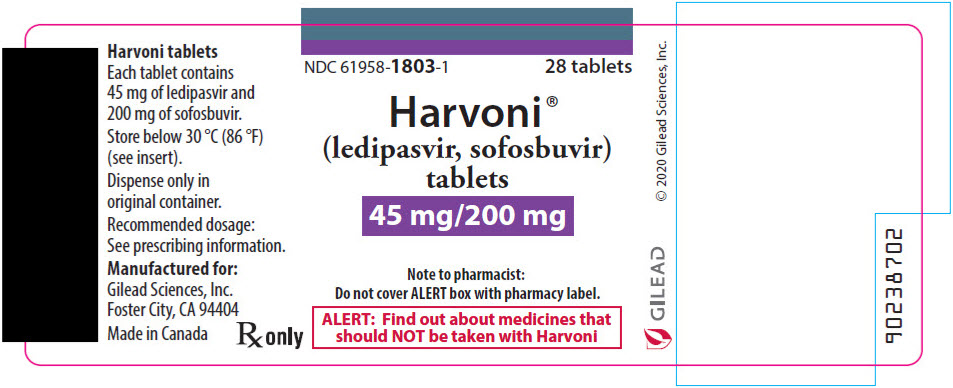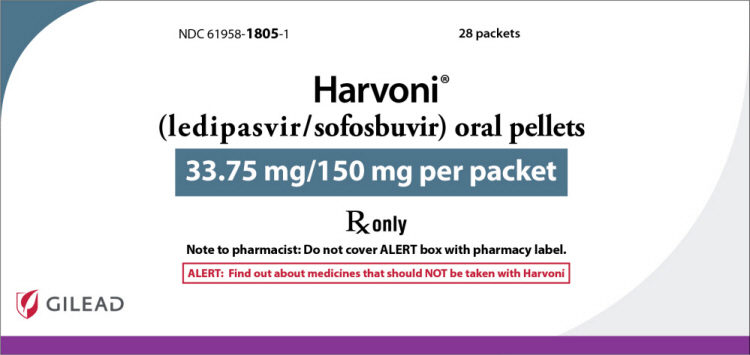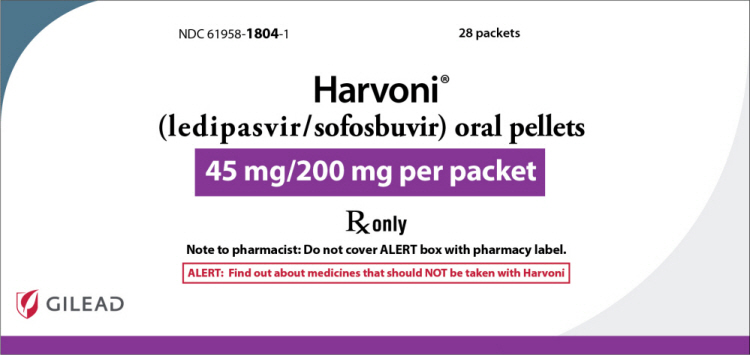 DRUG LABEL: Harvoni
NDC: 61958-1801 | Form: TABLET, FILM COATED
Manufacturer: Gilead Sciences, Inc
Category: prescription | Type: HUMAN PRESCRIPTION DRUG LABEL
Date: 20241226

ACTIVE INGREDIENTS: LEDIPASVIR 90 mg/1 1; SOFOSBUVIR 400 mg/1 1
INACTIVE INGREDIENTS: ALCOHOL; COPOVIDONE K25-31; LACTOSE MONOHYDRATE; MICROCRYSTALLINE CELLULOSE; SILICON DIOXIDE; CROSCARMELLOSE SODIUM; MAGNESIUM STEARATE; WATER; TITANIUM DIOXIDE; POLYETHYLENE GLYCOL 3350; TALC; FD&C YELLOW NO. 6; POLYVINYL ALCOHOL, UNSPECIFIED

HIGHLIGHTS OF PRESCRIBING INFORMATION

These highlights do not include all the information needed to use HARVONI® safely and effectively. See full prescribing information for HARVONI.
HARVONI® (ledipasvir and sofosbuvir) tablets, for oral use
HARVONI® (ledipasvir and sofosbuvir) oral pellets
Initial U.S. Approval: 2014

WARNING: RISK OF HEPATITIS B VIRUS REACTIVATION IN PATIENTS COINFECTED WITH HCV AND HBV

See full prescribing information for complete boxed warning.

Hepatitis B virus (HBV) reactivation has been reported, in some cases resulting in fulminant hepatitis, hepatic failure, and death. (5.1)

1 INDICATIONS AND USAGE

HARVONI is a fixed-dose combination of ledipasvir, a hepatitis C virus (HCV) NS5A inhibitor, and sofosbuvir, an HCV nucleotide analog NS5B polymerase inhibitor, and is indicated for the treatment of chronic hepatitis C virus (HCV) in adults and pediatric patients 3 years of age and older:

- Genotype 1, 4, 5, or 6 infection without cirrhosis or with compensated cirrhosis
- Genotype 1 infection with decompensated cirrhosis, in combination with ribavirin
- Genotype 1 or 4 infection who are liver transplant recipients without cirrhosis or with compensated cirrhosis, in combination with ribavirin. (1)

2 DOSAGE AND ADMINISTRATION

- Testing prior to the initiation of therapy: Test all patients for HBV infection by measuring HBsAg and anti-HBc. (2.1)
- Recommended treatment regimen and duration in patients 3 years of age and older: (2.2)

HCV Genotype | Patient Population | Regimen and Duration
Genotype 1 | Treatment-naïve without cirrhosis or with compensated cirrhosis (Child-Pugh A) | HARVONI 12 weeks
Genotype 1 | Treatment-experienced without cirrhosis | HARVONI 12 weeks
Genotype 1 | Treatment-experienced with compensated cirrhosis (Child-Pugh A) | HARVONI 24 weeks
Genotype 1 | Treatment-naïve and treatment-experienced with decompensated cirrhosis (Child-Pugh B or C) | HARVONI + ribavirin 12 weeks
Genotype 1 or 4 | Treatment-naïve and treatment-experienced liver transplant recipients without cirrhosis, or with compensated cirrhosis (Child-Pugh A) | HARVONI + ribavirin 12 weeks
Genotype 4, 5, or 6 | Treatment-naïve and treatment-experienced without cirrhosis or with compensated cirrhosis (Child-Pugh A) | HARVONI 12 weeks

- Recommended dosage in adults: One tablet (90 mg of ledipasvir and 400 mg of sofosbuvir) taken orally once daily with or without food. (2.3)
- Recommended dosage in pediatric patients 3 years and older: Recommended dosage of HARVONI in pediatric patients 3 years of age and older is based on weight. Refer to Table 2 of the full prescribing information for specific dosing guidelines based on body weight. (2.4)
- Instructions for Use should be followed for preparation and administration of HARVONI oral pellets. (2.5)
- HCV/HIV-1 coinfection: For adult and pediatric patients with HCV/HIV-1 coinfection, follow the dosage recommendations in the tables in the full prescribing information. (2.3, 2.4)
- If used in combination with ribavirin, follow the recommendations for ribavirin dosing and dosage modifications. (2.3, 2.4)
- For patients with any degree of renal impairment, including end stage renal disease on dialysis, no HARVONI dosage adjustment is recommended. (2.6)

3 DOSAGE FORMS AND STRENGTHS

- Tablets: 90 mg of ledipasvir and 400 mg of sofosbuvir; 45 mg of ledipasvir and 200 mg of sofosbuvir. (3)
- Oral Pellets: 45 mg of ledipasvir and 200 mg of sofosbuvir; 33.75 mg of ledipasvir and 150 mg of sofosbuvir. (3)

4 CONTRAINDICATIONS

If used in combination with ribavirin, all contraindications to ribavirin also apply to HARVONI combination therapy. (4)

5 WARNINGS AND PRECAUTIONS

- Risk of Hepatitis B Virus Reactivation: Test all patients for evidence of current or prior HBV infection before initiation of HCV treatment. Monitor HCV/HBV coinfected patients for HBV reactivation and hepatitis flare during HCV treatment and post-treatment follow-up. Initiate appropriate patient management for HBV infection as clinically indicated. (5.1)
- Bradycardia with amiodarone coadministration: Serious symptomatic bradycardia may occur in patients taking amiodarone, particularly in patients also receiving beta blockers, or those with underlying cardiac comorbidities and/or advanced liver disease. Coadministration of amiodarone with HARVONI is not recommended. In patients without alternative, viable treatment options, cardiac monitoring is recommended. (5.2, 6.2, 7.2)

6 ADVERSE REACTIONS

- The most common adverse reactions (incidence greater than or equal to 10%, all grades) observed with treatment with HARVONI were fatigue, headache, and asthenia. (6.1)

To report SUSPECTED ADVERSE REACTIONS, contact Gilead Sciences, Inc. at 1-800-GILEAD-5 or FDA at 1-800-FDA-1088 or www.fda.gov/medwatch.

7 DRUG INTERACTIONS

- Coadministration with amiodarone may result in serious symptomatic bradycardia. Use of HARVONI with amiodarone is not recommended. (5.2, 6.2, 7.2)
- P-gp inducers (e.g., rifampin, St. John's wort): May alter concentrations of ledipasvir and sofosbuvir. Use of HARVONI with P-gp inducers is not recommended. (5.3, 7, 12.3)
- Consult the full prescribing information prior to use for potential drug interactions. (5.2, 5.3, 7, 12.3)
- Clearance of HCV infection with direct acting antivirals may lead to changes in hepatic function, which may impact safe and effective use of concomitant medications. Frequent monitoring of relevant laboratory parameters (INR or blood glucose) and dose adjustments of certain concomitant medications may be necessary. (7.2)

8 USE IN SPECIFIC POPULATIONS

- Pediatric Use: No data are available regarding the safety of HARVONI in pediatric patients with renal impairment. (8.4)

FULL PRESCRIBING INFORMATION

WARNING: RISK OF HEPATITIS B VIRUS REACTIVATION IN PATIENTS COINFECTED WITH HCV AND HBV

Test all patients for evidence of current or prior hepatitis B virus (HBV) infection before initiating treatment with HARVONI. HBV reactivation has been reported in HCV/HBV coinfected patients who were undergoing or had completed treatment with HCV direct acting antivirals and were not receiving HBV antiviral therapy. Some cases have resulted in fulminant hepatitis, hepatic failure, and death. Monitor HCV/HBV coinfected patients for hepatitis flare or HBV reactivation during HCV treatment and post-treatment follow-up. Initiate appropriate patient management for HBV infection as clinically indicated [see Warnings and Precautions (5.1)].

1 INDICATIONS AND USAGE

HARVONI is indicated for the treatment of adults and pediatric patients 3 years of age and older with chronic hepatitis C virus (HCV) [see Dosage and Administration (2.2 and 2.3) and Clinical Studies (14)]:

- genotype 1, 4, 5, or 6 infection without cirrhosis or with compensated cirrhosis
- genotype 1 infection with decompensated cirrhosis, for use in combination with ribavirin
- genotype 1 or 4 infection who are liver transplant recipients without cirrhosis or with compensated cirrhosis, for use in combination with ribavirin

2 DOSAGE AND ADMINISTRATION

2.1 Testing Prior to the Initiation of Therapy

Test all patients for evidence of current or prior HBV infection by measuring hepatitis B surface antigen (HBsAg) and hepatitis B core antibody (anti-HBc) before initiating HCV treatment with HARVONI [see Warnings and Precautions (5.1)].

2.2 Recommended Treatment Regimen and Duration in Patients 3 Years of Age and Older with Genotype 1, 4, 5, or 6 HCV

Table 1 shows the recommended HARVONI treatment regimen and duration based on patient population. Relapse rates are affected by baseline host and viral factors and differ between treatment durations for certain subgroups [see Clinical Studies (14)].

For patients with HCV/HIV-1 coinfection, follow the dosage recommendations in Table 1 [see Clinical Studies (14)]. Refer to Drug Interactions (7) for dosage recommendations for concomitant HIV-1 antiviral drugs.

Table 1 Recommended Treatment Regimen and Duration for HARVONI in Patients 3 Years of Age and Older with Genotype 1, 4, 5, or 6 HCV
HCV Genotype | Patient Population | Treatment Regimen and Duration
Genotype 1 | Treatment-naïve without cirrhosis or with compensated cirrhosis (Child-Pugh A) | HARVONI 12 weeks [HARVONI for 8 weeks can be considered in treatment-naïve genotype 1 patients without cirrhosis who have pretreatment HCV RNA less than 6 million IU/mL [see Clinical Studies (14.2)].]
Genotype 1 | Treatment-experienced [Treatment-experienced adult and pediatric subjects have failed a peginterferon alfa +/- ribavirin based regimen with or without an HCV protease inhibitor.] without cirrhosis | HARVONI 12 weeks
Genotype 1 | Treatment-experienced with compensated cirrhosis (Child-Pugh A) | HARVONI 24 weeks [HARVONI + ribavirin for 12 weeks can be considered in treatment-experienced genotype 1 patients with cirrhosis who are eligible for ribavirin [see Dosage and Administration (2.3 and 2.4) and Clinical Studies (14.2)].]
Genotype 1 | Treatment-naïve and treatment-experienced with decompensated cirrhosis (Child-Pugh B or C) | HARVONI + ribavirin [See Dosage and Administration 2.3 and 2.4 for ribavirin dosage recommendations.] 12 weeks
Genotype 1 or 4 | Treatment-naïve and treatment-experienced liver transplant recipients without cirrhosis, or with compensated cirrhosis (Child-Pugh A) | HARVONI + ribavirin 12 weeks
Genotype 4, 5, or 6 | Treatment-naïve and treatment-experienced, without cirrhosis or with compensated cirrhosis (Child-Pugh A) | HARVONI 12 weeks

2.3 Recommended Dosage in Adults

The recommended dosage of HARVONI in adults with genotype 1, 4, 5, or 6 HCV is one tablet (90 mg ledipasvir and 400 mg sofosbuvir) taken orally once daily with or without food [see Clinical Pharmacology (12.3)].

The daily dosage of ribavirin is weight-based (1000 mg for patients <75 kg and 1200 mg for those ≥75 kg) administered orally in two divided doses with food.

In patients with decompensated cirrhosis, the starting dosage of ribavirin is 600 mg and can be titrated up to 1000 mg for patients <75 kg and 1200 mg for those ≥75 kg in two divided doses with food. If the starting dosage of ribavirin is not well tolerated, the dosage should be reduced as clinically indicated based on hemoglobin levels.

For further information on ribavirin dosing and dosage modifications, refer to the ribavirin prescribing information [see Dosage and Administration (2.4), Use in Specific Populations (8.6), and Clinical Studies (14.5)].

2.4 Recommended Dosage in Pediatric Patients 3 Years of Age and Older

The recommended dosage of HARVONI in pediatric patients 3 years of age and older with genotype 1, 4, 5, or 6 HCV using HARVONI tablets or oral pellets is based on weight (Table 2). Table 3 provides the weight-based dosage of ribavirin when used in combination with HARVONI for pediatric patients. Take HARVONI tablets or pellets (with or without food) once daily [see Dosage and Administration (2.5), Clinical Pharmacology (12.3), and Clinical Studies (14.7)]. HARVONI pellets can be taken in pediatric patients who cannot swallow the tablet formulation.

Table 2 Dosing for Pediatric Patients 3 Years and Older Using HARVONI Tablets or Oral Pellets
Body Weight (kg) | Dosing of HARVONI Tablets or Oral Pellets | HARVONI Daily Dose
at least 35 | one 90 mg/400 mg tablet once daily or two 45 mg/200 mg tablets once daily or two 45 mg/200 mg packets of pellets once daily | 90 mg/400 mg per day
17 to less than 35 | one 45 mg/200 mg tablet once daily or one 45 mg/200 mg packet of pellets once daily | 45 mg/200 mg per day
less than 17 | one 33.75 mg/150 mg packet of pellets once daily | 33.75 mg/150 mg per day

Table 3 Recommended Dosing for Ribavirin in Combination Therapy with HARVONI for Pediatric Patients 3 Years and Older
Body Weight (kg) | Oral Ribavirin Daily Dosage [The daily dosage of ribavirin is weight-based and is administered orally in two divided doses with food.]
less than 47 | 15 mg per kg per day (divided dose AM and PM)
47–49 | 600 mg per day (1 × 200 mg AM, 2 × 200 mg PM)
50–65 | 800 mg per day (2 × 200 mg AM, 2 × 200 mg PM)
66–80 | 1000 mg per day (2 × 200 mg AM, 3 × 200 mg PM)
greater than 80 | 1200 mg per day (3 × 200 mg AM, 3 × 200 mg PM)

2.5 Preparation and Administration of Oral Pellets

See the HARVONI oral pellets full Instructions for Use for details on the preparation and administration of HARVONI pellets.

Do not chew HARVONI pellets. If HARVONI pellets are administered with food, sprinkle the pellets on one or more spoonfuls of non-acidic soft food at or below room temperature. Examples of non-acidic foods include pudding, chocolate syrup, mashed potato, and ice cream. Take HARVONI pellets within 30 minutes of gently mixing with food and swallow the entire contents without chewing to avoid a bitter aftertaste.

2.6 Renal Impairment

No dosage adjustment of HARVONI is recommended in patients with any degree of renal impairment, including end stage renal disease (ESRD) on dialysis [see Dosage and Administration (2.3)]. Take HARVONI with or without ribavirin according to the recommendations in Table 1 [see Adverse Reactions (6.1), Use in Specific Populations (8.6), and Clinical Studies (14.6)]. Refer to ribavirin tablet prescribing information for ribavirin dosage modification for patients with CrCl less than or equal to 50 mL per minute.

3 DOSAGE FORMS AND STRENGTHS

HARVONI is available as tablets or pellets for oral use. Each dosage form is available in two dose strengths.

- 90 mg/400 mg Tablets: orange, diamond-shaped, film-coated tablet debossed with "GSI" on one side and "7985" on the other side of the tablet. Each tablet contains 90 mg ledipasvir and 400 mg sofosbuvir.
- 45 mg/200 mg Tablets: white, capsule-shaped, film-coated tablets, debossed with "GSI" on one side and "HRV" on the other side. Each tablet contains 45 mg ledipasvir and 200 mg sofosbuvir.
- 45 mg/200 mg Pellets: orange pellets in unit-dose packets. Each packet contains 45 mg ledipasvir and 200 mg sofosbuvir.
- 33.75 mg/150 mg Pellets: orange pellets in unit-dose packets. Each packet contains 33.75 mg ledipasvir and 150 mg sofosbuvir.

4 CONTRAINDICATIONS

If HARVONI is administered with ribavirin, the contraindications to ribavirin also apply to this combination regimen. Refer to the ribavirin prescribing information for a list of contraindications for ribavirin [see Dosage and Administration (2.2)].

5 WARNINGS AND PRECAUTIONS

5.1 Risk of Hepatitis B Virus Reactivation in Patients Coinfected with HCV and HBV

Hepatitis B virus (HBV) reactivation has been reported in HCV/HBV coinfected patients who were undergoing or had completed treatment with HCV direct acting antivirals, and who were not receiving HBV antiviral therapy. Some cases have resulted in fulminant hepatitis, hepatic failure, and death. Cases have been reported in patients who are HBsAg positive and also in patients with serologic evidence of resolved HBV infection (i.e., HBsAg negative and anti-HBc positive). HBV reactivation has also been reported in patients receiving certain immunosuppressants or chemotherapeutic agents; the risk of HBV reactivation associated with treatment with HCV direct-acting antivirals may be increased in these patients.

HBV reactivation is characterized as an abrupt increase in HBV replication manifesting as a rapid increase in serum HBV DNA level. In patients with resolved HBV infection, reappearance of HBsAg can occur. Reactivation of HBV replication may be accompanied by hepatitis, i.e., increases in aminotransferase levels and, in severe cases, increases in bilirubin levels, liver failure, and death can occur.

Test all patients for evidence of current or prior HBV infection by measuring HBsAg and anti-HBc before initiating HCV treatment with HARVONI. In patients with serologic evidence of HBV infection, monitor for clinical and laboratory signs of hepatitis flare or HBV reactivation during HCV treatment with HARVONI and during post-treatment follow-up. Initiate appropriate patient management for HBV infection as clinically indicated.

5.2 Serious Symptomatic Bradycardia When Coadministered with Amiodarone

Postmarketing cases of symptomatic bradycardia, as well as fatal cardiac arrest and cases requiring pacemaker intervention, have been reported when amiodarone is coadministered with HARVONI. Bradycardia has generally occurred within hours to days, but cases have been observed up to 2 weeks after initiating HCV treatment. Patients also taking beta blockers, or those with underlying cardiac comorbidities and/or advanced liver disease, may be at increased risk for symptomatic bradycardia with coadministration of amiodarone. Bradycardia generally resolved after discontinuation of HCV treatment. The mechanism for this effect is unknown.

Coadministration of amiodarone with HARVONI is not recommended. For patients taking amiodarone who have no other alternative, viable treatment options and who will be coadministered HARVONI:

- Counsel patients about the risk of serious symptomatic bradycardia
- Cardiac monitoring in an in-patient setting for the first 48 hours of coadministration is recommended, after which outpatient or self-monitoring of the heart rate should occur on a daily basis through at least the first 2 weeks of treatment.

Patients who are taking HARVONI who need to start amiodarone therapy due to no other alternative, viable treatment options should undergo similar cardiac monitoring as outlined above.

Due to amiodarone's long half-life, patients discontinuing amiodarone just prior to starting HARVONI should also undergo similar cardiac monitoring as outlined above.

Patients who develop signs or symptoms of bradycardia should seek medical evaluation immediately. Symptoms may include near-fainting or fainting, dizziness or lightheadedness, malaise, weakness, excessive tiredness, shortness of breath, chest pains, confusion, or memory problems [see Adverse Reactions (6.2), Drug Interactions (7.2)].

5.3 Risk of Reduced Therapeutic Effect Due to Use with P-gp Inducers

The concomitant use of HARVONI and P-gp inducers may significantly decrease ledipasvir and sofosbuvir plasma concentrations and may lead to a reduced therapeutic effect of HARVONI. Therefore, the use of HARVONI with P-gp inducers (e.g., rifampin, St. John's wort) is not recommended [see Drug Interactions (7.2)].

5.4 Risks Associated with Ribavirin Combination Treatment

If HARVONI is administered with ribavirin, the warnings and precautions for ribavirin, in particular the pregnancy avoidance warning, apply to this combination regimen. Refer to the ribavirin prescribing information for a full list of the warnings and precautions for ribavirin [see Dosage and Administration (2.2)].

6 ADVERSE REACTIONS

The following serious adverse reactions are described below and elsewhere in labeling:

- Serious Symptomatic Bradycardia When Coadministered with Amiodarone [see Warnings and Precautions (5.2)].

6.1 Clinical Trials Experience

Because clinical trials are conducted under widely varying conditions, adverse reaction rates observed in the clinical trials of a drug cannot be directly compared to rates in the clinical trials of another drug and may not reflect the rates observed in practice.

If HARVONI is administered with ribavirin to adults, refer to the prescribing information for ribavirin for a description of ribavirin-associated adverse reactions.

Clinical Trials in Adult Subjects

The safety assessment of HARVONI was based on pooled data from three randomized, open-label Phase 3 clinical trials (ION-3, ION-1, and ION-2) of subjects with genotype 1 HCV with compensated liver disease (with and without cirrhosis) including 215, 539, and 326 subjects who received HARVONI once daily by mouth for 8, 12, and 24 weeks, respectively [see Clinical Studies (14)].

The proportion of subjects who permanently discontinued treatment due to adverse events was 0%, less than 1%, and 1% for subjects receiving HARVONI for 8, 12, and 24 weeks, respectively.

The most common adverse reactions (at least 10%) were fatigue and headache in subjects treated with 8, 12, or 24 weeks of HARVONI.

Table 4 lists adverse reactions (adverse events assessed as causally related by the investigator, all grades) observed in at least 5% of subjects receiving 8, 12, or 24 weeks of treatment with HARVONI in clinical trials. The majority of adverse reactions presented in Table 4 occurred at severity of grade 1. The side-by-side tabulation is to simplify presentation; direct comparison across trials should not be made due to differing trial designs.

Table 4 Adverse Reactions (All Grades) Reported in ≥5% of Subjects Receiving 8, 12, or 24 Weeks of Treatment with HARVONI
 | HARVONI 8 weeks (N=215) | HARVONI 12 weeks (N=539) | HARVONI 24 weeks (N=326)
Fatigue | 16% | 13% | 18%
Headache | 11% | 14% | 17%
Nausea | 6% | 7% | 9%
Diarrhea | 4% | 3% | 7%
Insomnia | 3% | 5% | 6%

The safety assessment of HARVONI was also based on pooled data from three open-label trials (Study 1119, ION-4, and ELECTRON-2) in 118 subjects with chronic HCV genotype 4, 5, or 6 infection with compensated liver disease (with or without cirrhosis) [see Clinical Studies (14.3)]. The subjects received HARVONI once daily by mouth for 12 weeks. The safety profile in subjects with chronic HCV genotype 4, 5, or 6 infection with compensated liver disease was similar to that observed in subjects with chronic HCV genotype 1 infection with compensated liver disease. The most common adverse reactions occurring in at least 10% of subjects were asthenia (18%), headache (14%), and fatigue (10%).

Adverse Reactions in Subjects with Cirrhosis

The safety assessment of HARVONI with or without ribavirin was based on a randomized, double-blind and placebo-controlled trial in treatment-experienced genotype 1 subjects with compensated cirrhosis and was compared to placebo in the SIRIUS trial. Subjects were randomized to receive 24 weeks of HARVONI once daily by mouth without ribavirin or 12 weeks of placebo followed by 12 weeks of HARVONI once daily by mouth + ribavirin [see Clinical Studies (14.2)]. Table 5 presents the adverse reactions, as defined above, that occurred with at least 5% greater frequency in subjects treated with 24 weeks of HARVONI or 12 weeks of HARVONI + ribavirin, compared to those reported for 12 weeks of placebo. The majority of the adverse reactions presented in Table 5 were Grade 1 or 2 in severity.

Table 5 Adverse Reactions with ≥5% Greater Frequency Reported in Treatment-Experienced Subjects with Cirrhosis Receiving HARVONI for 24 Weeks or HARVONI + Ribavirin for 12 Weeks Compared to Placebo for 12 weeks
 | HARVONI 24 weeks (N=78) | HARVONI + RBV 12 weeks (N=76) | Placebo 12 weeks (N=77)
Asthenia | 31% | 36% | 23%
Headache | 29% | 13% | 16%
Fatigue | 18% | 4% | 1%
Cough | 5% | 11% | 1%
Myalgia | 9% | 4% | 0
Dyspnea | 3% | 9% | 1%
Irritability | 8% | 7% | 1%
Dizziness | 5% | 1% | 0
RBV=ribavirin

Adverse Reactions in Subjects Coinfected with HIV-1

The safety assessment of HARVONI was based on an open-label clinical trial in 335 genotype 1 or 4 subjects with HCV/HIV-1 coinfection who were on stable antiretroviral therapy in Study ION-4 [see Clinical Studies (14.4)]. The safety profile in HCV/HIV-1 coinfected subjects was similar to that observed in HCV mono-infected subjects. The most common adverse reactions occurring in at least 10% of subjects were headache (20%) and fatigue (17%).

Adverse Reactions in Liver Transplant Recipients and/or Subjects with Decompensated Cirrhosis

The safety assessment of HARVONI with ribavirin in liver transplant recipients and/or those who had decompensated liver disease was based on pooled data from two Phase 2 open-label clinical trials including 336 subjects who received HARVONI plus ribavirin for 12 weeks. Subjects with Child-Pugh-Turcotte (CPT) scores greater than 12 were excluded from the trials [see Clinical Studies (14.5)].

The adverse events observed were consistent with the expected clinical sequelae of liver transplantation and/or decompensated liver disease, or the known safety profile of HARVONI and/or ribavirin.

Decreases in hemoglobin to less than 10 g/dL and 8.5 g/dL during treatment were observed in 38% and 13% of subjects treated with HARVONI plus ribavirin for 12 weeks, respectively. Ribavirin was permanently discontinued in 11% of subjects treated with HARVONI plus ribavirin for 12 weeks.

Liver Transplant Recipients with Compensated Liver Disease:

Among the 174 liver transplant recipients with compensated liver disease who received HARVONI with ribavirin for 12 weeks, 2 (1%) subjects permanently discontinued HARVONI due to an adverse event.

Subjects with Decompensated Liver Disease:

Among the 162 subjects with decompensated liver disease (pre- or post-transplant) who received HARVONI with ribavirin for 12 weeks, 7 (4%) subjects died, 4 (2%) subjects underwent liver transplantation, and 1 subject (<1%) underwent liver transplantation and died during treatment or within 30 days after discontinuation of treatment. Because these events occurred in patients with advanced liver disease who are at risk of progression of liver disease including liver failure and death, it is not possible to reliably assess the contribution of drug effect to outcomes. A total of 4 (2%) subjects permanently discontinued HARVONI due to an adverse event.

Less Common Adverse Reactions Reported in Clinical Trials (less than 5%): The following adverse reactions occurred in less than 5% of subjects receiving HARVONI in any one trial. These events have been included because of their seriousness or assessment of potential causal relationship.

Psychiatric disorders: depression (including in subjects with pre-existing history of psychiatric illness).

Depression (particularly in subjects with pre-existing history of psychiatric illness) occurred in subjects receiving sofosbuvir containing regimens. Suicidal ideation and suicide have occurred in less than 1% of subjects treated with sofosbuvir in combination with ribavirin or pegylated interferon/ribavirin in other clinical trials.

Laboratory Abnormalities

Bilirubin Elevations: Bilirubin elevations of greater than 1.5×ULN were observed in 3%, less than 1%, and 2% of subjects treated with HARVONI for 8, 12, and 24 weeks, respectively. Bilirubin elevations of greater than 1.5×ULN were observed in 3%, 11%, and 3% of subjects with compensated cirrhosis treated with placebo, HARVONI + ribavirin for 12 weeks, and HARVONI for 24 weeks, respectively, in the SIRIUS trial.

Lipase Elevations: Transient, asymptomatic lipase elevations of greater than 3×ULN were observed in less than 1%, 2%, and 3% of subjects treated with HARVONI for 8, 12, and 24 weeks, respectively. Transient, asymptomatic lipase elevations of greater than 3× ULN were observed in 1%, 3%, and 9% of subjects with compensated cirrhosis treated with placebo, HARVONI + ribavirin for 12 weeks, and HARVONI for 24 weeks, respectively, in the SIRIUS trial.

Creatine Kinase: Creatine kinase was not assessed in Phase 3 trials ION-3, ION-1, or ION-2 of HARVONI. Creatine kinase was assessed in the ION-4 trial. Isolated, asymptomatic creatine kinase elevations of greater than or equal to 10×ULN was observed in 1% of subjects treated with HARVONI for 12 weeks in the ION-4 trial and has also been previously reported in subjects treated with sofosbuvir in combination with ribavirin or peginterferon/ribavirin in other clinical trials.

Adverse Reactions in Adults with Severe Renal Impairment, Including those on Dialysis

In an open-label trial (Trial 0154) in which adults with HCV with compensated liver disease (with or without cirrhosis) and severe renal impairment received HARVONI for 12 weeks (N=18), the most common adverse reaction was fatigue (17%) [see Clinical Studies (14.6)].

In an open-label clinical trial, Trial 4063, a total of 95 adults with HCV with compensated liver disease (with or without cirrhosis) and ESRD requiring dialysis received HARVONI for 8 (n=45), 12 (n=31), or 24 (n=19) weeks. The most common adverse reactions were insomnia and headache (each reported in 4% of subjects overall) [see Clinical Studies (14.6)].

Adverse Reactions in Pediatric Subjects 3 Years of Age and Older

The safety assessment of HARVONI in pediatric subjects 3 years of age and older is based on data from a Phase 2, open-label clinical trial (Study 1116). In total, 226 subjects were enrolled, which included 223 subjects without cirrhosis or with compensated cirrhosis who were treated with HARVONI for 12 weeks; one genotype 1 treatment-experienced subject with cirrhosis who was treated with HARVONI for 24 weeks; and two genotype 3 subjects who were treated with HARVONI + ribavirin for 24 weeks. The adverse reactions observed were consistent with those observed in clinical studies of HARVONI in adults. Limited safety data are available in pediatric subjects receiving HARVONI for 24 weeks. No Grade 3 or 4 adverse reactions or discontinuation due to an adverse reaction was observed in those pediatric subjects receiving HARVONI for 24 weeks [see Clinical Studies (14.7)].

In a 5-year follow-up study, 178 of the 226 subjects from the Phase 2 open-label clinical trial (Study 1116) were followed for a median (Q1, Q3) duration of 239 (143, 244) weeks. No notable effects on growth as assessed by changes from baseline through end of study were observed for height, weight, BMI percentiles, and Z-scores for any age group. No notable effects were observed on the development of secondary sexual characteristics of subjects as assessed by changes from baseline through end of study in Tanner pubertal stages [see Use in Specific Populations (8.4)].

6.2 Postmarketing Experience

The following adverse reactions have been identified during post approval use of HARVONI. Because postmarketing reactions are reported voluntarily from a population of uncertain size, it is not always possible to reliably estimate their frequency or establish a causal relationship to drug exposure.

Cardiac Disorders

Serious symptomatic bradycardia has been reported in patients taking amiodarone who initiate treatment with HARVONI [see Warnings and Precautions (5.2), Drug Interactions (7.2)].

Skin and Subcutaneous Tissue Disorders

Skin rashes, sometimes with blisters or angioedema-like swelling

Angioedema

7 DRUG INTERACTIONS

7.1 Potential for Drug Interaction

As HARVONI contains ledipasvir and sofosbuvir, any interactions that have been identified with these agents individually may occur with HARVONI.

After oral administration of HARVONI, sofosbuvir is rapidly absorbed and subject to extensive first-pass hepatic extraction. In clinical pharmacology studies, both sofosbuvir and the inactive metabolite GS-331007 were monitored for purposes of pharmacokinetic analyses.

Ledipasvir is an inhibitor of the drug transporters P-gp and breast cancer resistance protein (BCRP) and may increase intestinal absorption of coadministered substrates for these transporters.

Ledipasvir and sofosbuvir are substrates of drug transporters P-gp and BCRP while GS-331007 is not. P-gp inducers (e.g., rifampin, St. John's wort) may decrease ledipasvir and sofosbuvir plasma concentrations, leading to reduced therapeutic effect of HARVONI, and the use with P-gp inducers is not recommended with HARVONI [see Warnings and Precautions (5.3)].

7.2 Established and Potentially Significant Drug Interactions

Clearance of HCV infection with direct acting antivirals may lead to changes in hepatic function, which may impact the safe and effective use of concomitant medications. For example, altered blood glucose control resulting in serious symptomatic hypoglycemia has been reported in diabetic patients in postmarketing case reports and published epidemiological studies. Management of hypoglycemia in these cases required either discontinuation or dose modification of concomitant medications used for diabetes treatment.

Frequent monitoring of relevant laboratory parameters (e.g., International Normalized Ratio [INR] in patients taking warfarin, blood glucose levels in diabetic patients) or drug concentrations of concomitant medications such as cytochrome P450 substrates with a narrow therapeutic index (e.g., certain immunosuppressants) is recommended to ensure safe and effective use. Dose adjustments of concomitant medications may be necessary.

Table 6 provides a listing of established or potentially clinically significant drug interactions. The drug interactions described are based on studies conducted with either HARVONI, the components of HARVONI (ledipasvir and sofosbuvir) as individual agents, or are predicted drug interactions that may occur with HARVONI [see Warnings and Precautions (5.2, 5.3) and Clinical Pharmacology (12.3)].

Table 6 Potentially Significant Drug Interactions: Alteration in Dose or Regimen May Be Recommended Based on Drug Interaction Studies or Predicted Interaction [This table is not all inclusive.]
Concomitant Drug Class: Drug Name | Effect on Concentration [↓ = decrease, ↑ = increase] | Clinical Comment
Acid Reducing Agents: | ↓ ledipasvir | Ledipasvir solubility decreases as pH increases. Drugs that increase gastric pH are expected to decrease concentration of ledipasvir.
Antacids (e.g., aluminum and magnesium hydroxide) | ↓ ledipasvir | It is recommended to separate antacid and HARVONI administration by 4 hours.
H2-receptor antagonists [These interactions have been studied in healthy adults.] (e.g., famotidine) | ↓ ledipasvir | H2-receptor antagonists may be administered simultaneously with or 12 hours apart from HARVONI at a dose that does not exceed doses comparable to famotidine 40 mg twice daily.
Proton-pump inhibitors (e.g., omeprazole) | ↓ ledipasvir | Proton-pump inhibitor doses comparable to omeprazole 20 mg or lower can be administered simultaneously with HARVONI under fasted conditions.
Antiarrhythmics: amiodarone | Effect on amiodarone, ledipasvir, and sofosbuvir concentrations unknown | Coadministration of amiodarone with HARVONI may result in serious symptomatic bradycardia. The mechanism of this effect is unknown. Coadministration of amiodarone with HARVONI is not recommended; if coadministration is required, cardiac monitoring is recommended [see Warnings and Precautions (5.2), Adverse Reactions (6.2)].
digoxin | ↑ digoxin | Coadministration of HARVONI with digoxin may increase the concentration of digoxin. Therapeutic concentration monitoring of digoxin is recommended when coadministered with HARVONI.
Anticonvulsants: carbamazepine phenytoin phenobarbital | ↓ ledipasvir ↓ sofosbuvir | Coadministration of HARVONI with carbamazepine, phenytoin, or phenobarbital is expected to decrease the concentration of ledipasvir and sofosbuvir, leading to reduced therapeutic effect of HARVONI. Coadministration is not recommended.
Antimycobacterials: rifabutin rifampin rifapentine | ↓ ledipasvir ↓ sofosbuvir | Coadministration of HARVONI with rifampin, rifabutin, or rifapentine is not recommended [see Warnings and Precautions (5.3)].
HIV Antiretrovirals:
Regimens containing tenofovir DF without an HIV protease inhibitor/ ritonavir or cobicistat | ↑ tenofovir | Monitor for tenofovir-associated adverse reactions in patients receiving HARVONI concomitantly with a regimen containing tenofovir DF without an HIV protease inhibitor/ritonavir or cobicistat. Refer to VIREAD or TRUVADA prescribing information for recommendations on renal monitoring.
Regimens containing tenofovir DF and an HIV protease inhibitor/ ritonavir or cobicistat; - atazanavir/ritonavir or cobicistat + emtricitabine/tenofovir DF - darunavir/ritonavir or cobicistat + emtricitabine/tenofovir DF - lopinavir/ritonavir + emtricitabine/tenofovir DF | ↑ tenofovir | The safety of increased tenofovir concentrations in the setting of HARVONI and an HIV protease inhibitor/ritonavir or cobicistat has not been established. Consider alternative HCV or antiretroviral therapy to avoid increases in tenofovir exposures. If coadministration is necessary, monitor for tenofovir-associated adverse reactions. Refer to VIREAD or TRUVADA prescribing information for recommendations on renal monitoring.
elvitegravir, cobicistat, emtricitabine, tenofovir DF | ↑ tenofovir | The safety of increased tenofovir concentrations in the setting of HARVONI and the combination of elvitegravir, cobicistat, emtricitabine, and tenofovir DF has not been established. Coadministration is not recommended.
tipranavir/ritonavir | ↓ ledipasvir ↓ sofosbuvir | Coadministration of HARVONI with tipranavir/ritonavir is expected to decrease the concentration of ledipasvir and sofosbuvir, leading to reduced therapeutic effect of HARVONI. Coadministration is not recommended.
HCV Products: simeprevir | ↑ ledipasvir ↑ simeprevir | Concentrations of ledipasvir and simeprevir are increased when simeprevir is coadministered with ledipasvir. Coadministration of HARVONI with simeprevir is not recommended.
Herbal Supplements: St. John's wort (Hypericum perforatum) | ↓ ledipasvir ↓ sofosbuvir | Coadministration of HARVONI with St. John's wort, a P-gp inducer, is not recommended [see Warnings and Precautions (5.3)].
HMG-CoA Reductase Inhibitors: rosuvastatin | ↑ rosuvastatin | Coadministration of HARVONI with rosuvastatin may significantly increase the concentration of rosuvastatin, which is associated with increased risk of myopathy, including rhabdomyolysis. Coadministration of HARVONI with rosuvastatin is not recommended.
atorvastatin | ↑ atorvastatin | Coadministration of HARVONI with atorvastatin may be associated with increased risk of myopathy, including rhabdomyolysis. Monitor closely for HMG-CoA reductase inhibitor-associated adverse reactions, such as myopathy and rhabdomyolysis.
tenofovir DF = tenofovir disoproxil fumarate

7.3 Drugs without Clinically Significant Interactions with HARVONI

Based on drug interaction studies conducted with the components of HARVONI (ledipasvir or sofosbuvir) or HARVONI, no clinically significant drug interactions have been either observed or are expected when HARVONI is used with the following drugs [see Clinical Pharmacology (12.3)]: abacavir, atazanavir/ritonavir, cyclosporine, darunavir/ritonavir, dolutegravir, efavirenz, elvitegravir/cobicistat/emtricitabine/tenofovir alafenamide, emtricitabine, lamivudine, methadone, midazolam, oral contraceptives, pravastatin, raltegravir, rilpivirine, tacrolimus, or verapamil. See Table 6 for use of HARVONI with certain HIV antiretroviral regimens [see Drug Interactions (7.2)].

8 USE IN SPECIFIC POPULATIONS

8.1 Pregnancy

Risk Summary

If HARVONI is administered with ribavirin, the combination regimen is contraindicated in pregnant women and in men whose female partners are pregnant. Refer to the ribavirin prescribing information for more information on ribavirin-associated risks of use during pregnancy.

No adequate human data are available to establish whether or not HARVONI poses a risk to pregnancy outcomes. In animal reproduction studies, no evidence of adverse developmental outcomes was observed with the components of HARVONI (ledipasvir or sofosbuvir) at exposures greater than those in humans at the recommended human dose (RHD) [see Data]. During organogenesis in the rat and rabbit, systemic exposures (AUC) to ledipasvir were approximately 4 (rats) and 2 (rabbits) times the exposure in humans at the RHD, while exposures to the predominant circulating metabolite of sofosbuvir (GS-331007) were ≥3 (rats) and 7 (rabbits) times the exposure in humans at the RHD. In rat pre/postnatal development studies, maternal systemic exposures (AUC) to ledipasvir and GS-331007 were approximately 5 and 7 times, respectively, the exposure in humans at the RHD.

The background risk of major birth defects and miscarriage for the indicated population is unknown. In the U.S. general population, the estimated background risk of major birth defects and miscarriage in clinically recognized pregnancies is 2–4% and 15–20%, respectively.

Data

Animal Data

Ledipasvir: Ledipasvir was administered orally to pregnant rats (up to 100 mg/kg/day) and rabbits (up to 180 mg/kg/day) on gestation days 6 to 18 and 7 to 20, respectively, and also to rats (oral doses up to 100 mg/kg/day) on gestation day 6 to lactation/post-partum day 20. No significant effects on embryo-fetal (rats and rabbits) or pre/postnatal (rats) development were observed at the highest doses tested. Systemic exposures (AUC) to ledipasvir were ≥4 (rats) and 2 (rabbits) times the exposure in humans at the RHD.

Sofosbuvir: Sofosbuvir was administered orally to pregnant rats (up to 500 mg/kg/day) and rabbits (up to 300 mg/kg/day) on gestation days 6 to 18 and 6 to 19, respectively, and also to rats (oral doses up to 500 mg/kg/day) on gestation day 6 to lactation/post-partum day 20. No significant effects on embryo-fetal (rats and rabbits) or pre/postnatal (rats) development were observed at the highest doses tested. Systemic exposures (AUC) to the predominant circulating metabolite of sofosbuvir (GS-331007) were ≥3 (rats) and 7 (rabbits) times the exposure in humans at the RHD, with exposures increasing during gestation from approximately 3 to 6 (rats) and 7 to 17 (rabbits) times the exposure in humans at the RHD.

8.2 Lactation

Risk Summary

It is not known whether ledipasvir or sofosbuvir, the components of HARVONI, or their metabolites are present in human breast milk, affect human milk production or have effects on the breastfed infant. When administered to lactating rats, ledipasvir was detected in the plasma of nursing pups likely due to the presence of ledipasvir in milk, without clear effects on nursing pups [see Data]. The predominant circulating metabolite of sofosbuvir (GS-331007) was the primary component observed in the milk of lactating rats, without effect on nursing pups.

The development and health benefits of breastfeeding should be considered along with the mother's clinical need for HARVONI and any potential adverse effects on the breastfed child from HARVONI or from the underlying maternal condition.

If HARVONI is administered with ribavirin, the nursing mother's information for ribavirin also applies to this combination regimen. Refer to the ribavirin prescribing information for more information on use during lactation.

Data

Ledipasvir: No effects of ledipasvir on growth and postnatal development were observed in nursing pups at the highest dose tested in rats. Maternal systemic exposure (AUC) to ledipasvir was approximately 5 times the exposure in humans at the RHD. Although not measured directly, ledipasvir was likely present in the milk of lactating rats, since systemic exposure (AUC) to ledipasvir of approximately 25% that of maternal exposure was observed in nursing pups on lactation day 10.

Sofosbuvir: No effects of sofosbuvir on growth and postnatal development were observed in nursing pups at the highest dose tested in rats. Maternal systemic exposure (AUC) to the predominant circulating metabolite of sofosbuvir (GS-331007) was approximately 7 times the exposure in humans at the RHD, with exposure of approximately 2% that of maternal exposure observed in nursing pups on lactation day 10. In a lactation study, sofosbuvir metabolites (primarily GS-331007) were excreted into the milk of lactating rats following administration of a single oral dose of sofosbuvir (20 mg/kg) on lactation day 2, with milk concentrations of approximately 10% that of maternal plasma concentrations observed 1 hour post-dose.

8.3 Females and Males of Reproductive Potential

If HARVONI is administered with ribavirin, the information for ribavirin with regard to pregnancy testing, contraception, and infertility also applies to this combination regimen. Refer to ribavirin prescribing information for additional information.

8.4 Pediatric Use

The safety, pharmacokinetics, and efficacy of HARVONI for treatment of HCV genotype 1 and 4 infection in treatment-naïve and treatment-experienced pediatric patients 3 years of age and older without cirrhosis or with compensated cirrhosis have been established in an open-label, multicenter clinical trial (Study 1116, N=226; 186 treatment-naïve, 40 treatment-experienced) and are comparable to that observed in adults.

The safety and efficacy of HARVONI for treatment of HCV genotypes 5 or 6 infection in pediatric patients 3 years of age and older are supported by comparable ledipasvir, sofosbuvir, and GS-331007 exposures between adults and pediatric patients [see Dosage and Administration (2.2 and 2.4), Adverse Reactions (6.1), Clinical Pharmacology (12.3), and Clinical Studies (14.3, 14.6, 14.7)]. Similar rationale is used to support dosing recommendations for pediatric patients with HCV genotype 1 infection who have decompensated cirrhosis (Child-Pugh B or C) and for pediatric patients with HCV genotype 1 and 4 infection who are liver transplant recipients without cirrhosis or with compensated cirrhosis.

In patients with severe renal impairment, including those requiring dialysis, exposures of GS-331007, the inactive metabolite of sofosbuvir, are increased [see Clinical Pharmacology (12.3)]. No data are available regarding the safety of HARVONI in pediatric patients with renal impairment [see Use in Specific Populations (8.6)].

The safety and efficacy of HARVONI have not been established in pediatric patients less than 3 years of age.

In a 5-year follow-up study, the long-term effects of HARVONI on pediatric growth were assessed in 178 pediatric subjects 3 years of age and older treated with HARVONI in Study 1116. No notable effects on growth from baseline through end of study were observed [see Adverse Reactions (6.1)]. All subjects who had achieved SVR12 maintained SVR through end of study.

8.5 Geriatric Use

Clinical trials of HARVONI included 225 subjects aged 65 and over (9% of total number of subjects in the clinical studies). No overall differences in safety or effectiveness were observed between these subjects and younger subjects, and other reported clinical experience has not identified differences in responses between the elderly and younger patients, but greater sensitivity of some older individuals cannot be ruled out. No dosage adjustment of HARVONI is warranted in geriatric patients [see Clinical Pharmacology (12.3)].

8.6 Renal Impairment

No dosage adjustment of HARVONI is recommended for patients with mild, moderate, or severe renal impairment, including ESRD requiring dialysis [see Dosage and Administration (2.4), Adverse Reactions (6.1), Clinical Pharmacology (12.3), and Clinical Studies (14.6)]. No safety data are available in subjects with both decompensated cirrhosis and severe renal impairment, including those on dialysis. Additionally, no safety data are available in pediatric patients with renal impairment [see Use in Specific Populations (8.4)]. Refer to ribavirin tablet prescribing information regarding use in patients with renal impairment.

8.7 Hepatic Impairment

No dosage adjustment of HARVONI is recommended for patients with mild, moderate, or severe hepatic impairment (Child-Pugh Class A, B, or C) [see Dosage and Administration (2.3), Clinical Pharmacology (12.3) and Clinical Studies (14.5)].

Clinical and hepatic laboratory monitoring, as clinically indicated, is recommended for patients with decompensated cirrhosis receiving treatment with HARVONI and ribavirin [see Adverse Reactions (6.1)].

10 OVERDOSAGE

No specific antidote is available for overdose with HARVONI. If overdose occurs, the patient must be monitored for evidence of toxicity. Treatment of overdose with HARVONI consists of general supportive measures including monitoring of vital signs as well as observation of the clinical status of the patient. Hemodialysis is unlikely to result in significant removal of ledipasvir since ledipasvir is highly bound to plasma protein. Hemodialysis can efficiently remove the predominant circulating metabolite of sofosbuvir, GS-331007, with an extraction ratio of 53%.

11 DESCRIPTION

Tablets

HARVONI tablets are fixed-dose combination tablets containing ledipasvir and sofosbuvir for oral administration. Ledipasvir is an HCV NS5A inhibitor and sofosbuvir is a nucleotide analog inhibitor of HCV NS5B polymerase.

Each 90 mg/400 mg tablet contains 90 mg ledipasvir and 400 mg sofosbuvir. The tablets include the following inactive ingredients: colloidal silicon dioxide, copovidone, croscarmellose sodium, lactose monohydrate, magnesium stearate, and microcrystalline cellulose. The tablets are film-coated with a coating material containing the following inactive ingredients: FD&C yellow #6/sunset yellow FCF aluminum lake, polyethylene glycol, polyvinyl alcohol, talc, and titanium dioxide.

Each 45 mg/200 mg tablet contains 45 mg ledipasvir and 200 mg sofosbuvir. The tablets include the following inactive ingredients: colloidal silicon dioxide, copovidone, croscarmellose sodium, lactose monohydrate, magnesium stearate, and microcrystalline cellulose. The tablets are film-coated with a coating material containing the following inactive ingredients: polyethylene glycol, polyvinyl alcohol, talc, and titanium dioxide.

Pellets

HARVONI oral pellets are for oral administration, supplied as small, orange pellets in unit-dose packets. Each unit-dose of HARVONI oral pellets contains either 45 mg ledipasvir and 200 mg sofosbuvir or 33.75 mg ledipasvir and 150 mg sofosbuvir and the following inactive ingredients: amino-methacrylate copolymer, colloidal silicon dioxide, copovidone, croscarmellose sodium, hypromellose, lactose monohydrate, iron oxide red, iron oxide yellow, magnesium stearate, microcrystalline cellulose, polyethylene glycol, talc, and titanium dioxide.

Ledipasvir: The IUPAC name for ledipasvir is methyl [(2S)-1-{(6S)-6-[5-(9,9-difluoro-7-{2-[(1R,3S,4S)-2-{(2S)-2-[(methoxycarbonyl)amino]-3-methylbutanoyl}-2-azabicyclo[2.2.1]hept-3-yl]-1H-benzimidazol-6-yl}-9H-fluoren-2-yl)-1H-imidazol-2-yl]-5-azaspiro[2.4]hept-5-yl}-3-methyl-1-oxobutan-2-yl]carbamate.

It has a molecular formula of C49H54F2N8O6 and a molecular weight of 889.00. It has the following structural formula:

Ledipasvir is practically insoluble (less than 0.1 mg/mL) across the pH range of 3.0–7.5 and is slightly soluble below pH 2.3 (1.1 mg/mL).

Sofosbuvir: The IUPAC name for sofosbuvir is (S)-isopropyl 2-((S)-(((2R,3R,4R,5R)-5-(2,4-dioxo-3,4-dihydropyrimidin-1(2H)-yl)-4-fluoro-3-hydroxy-4-methyltetrahydrofuran-2-yl)methoxy)-(phenoxy)phosphorylamino)propanoate. It has a molecular formula of C22H29FN3O9P and a molecular weight of 529.45. It has the following structural formula:

Sofosbuvir is a white to off-white crystalline solid with a solubility of at least 2 mg/mL across the pH range of 2–7.7 at 37°C and is slightly soluble in water.

12 CLINICAL PHARMACOLOGY

12.1 Mechanism of Action

HARVONI is a fixed-dose combination of ledipasvir and sofosbuvir, which are direct-acting antiviral agents against the hepatitis C virus [see Microbiology (12.4)].

12.2 Pharmacodynamics

Cardiac Electrophysiology

Thorough QT studies have been conducted for ledipasvir and sofosbuvir.

The effect of ledipasvir 120 mg twice daily (2.67 times the maximum recommended dosage) for 10 days on QTc interval was evaluated in a randomized, multiple-dose, placebo-, and active-controlled (moxifloxacin 400 mg) three-period crossover thorough QT trial in 59 healthy subjects. At the dose of 120 mg twice daily (2.67 times the maximum recommended dosage), ledipasvir does not prolong QTc interval to any clinically relevant extent.

The effect of sofosbuvir 400 mg (maximum recommended dosage) and 1200 mg (three times the maximum recommended dosage) on QTc interval was evaluated in a randomized, single-dose, placebo-, and active-controlled (moxifloxacin 400 mg) four-period crossover thorough QT trial in 59 healthy subjects. At a dose three times the maximum recommended dose, sofosbuvir does not prolong QTc to any clinically relevant extent.

12.3 Pharmacokinetics

Absorption

The pharmacokinetic properties of ledipasvir, sofosbuvir, and the predominant circulating metabolite GS-331007 have been evaluated in healthy adult subjects and in subjects with chronic hepatitis C. Following oral administration of HARVONI, ledipasvir median peak concentrations were observed 4 to 4.5 hours post-dose. Sofosbuvir was absorbed quickly and the peak median plasma concentration was observed ~0.8 to 1 hour post-dose. Median peak plasma concentration of GS-331007 was observed between 3.5 to 4 hours post-dose.

Based on the population pharmacokinetic analysis in HCV-infected subjects, geometric mean steady-state AUC0–24 for ledipasvir (N=2113), sofosbuvir (N=1542), and GS-331007 (N=2113) were 7290, 1320, and 12,000 ng∙hr/mL, respectively. Steady-state Cmax for ledipasvir, sofosbuvir, and GS-331007 were 323, 618, and 707 ng/mL, respectively. Sofosbuvir and GS-331007 AUC0–24 and Cmax were similar in healthy adult subjects and subjects with HCV infection. Relative to healthy subjects (N=191), ledipasvir AUC0–24 and Cmax were 24% lower and 32% lower, respectively, in HCV-infected subjects.

Effect of Food

Relative to fasting conditions, the administration of a single dose of HARVONI with a moderate fat (~600 kcal, 25% to 30% fat) or high fat (~1000 kcal, 50% fat) meal increased sofosbuvir AUC0–inf by approximately 2-fold, but did not significantly affect sofosbuvir Cmax. The exposures of GS-331007 and ledipasvir were not altered in the presence of either meal type. The response rates in Phase 3 trials were similar in HCV-infected subjects who received HARVONI with food or without food. HARVONI can be administered without regard to food.

Distribution

Ledipasvir is greater than 99.8% bound to human plasma proteins. After a single 90 mg dose of [^14C]-ledipasvir in healthy subjects, the blood to plasma ratio of ^14C-radioactivity ranged between 0.51 and 0.66.

Sofosbuvir is approximately 61–65% bound to human plasma proteins and the binding is independent of drug concentration over the range of 1 microgram/mL to 20 microgram/mL. Protein binding of GS-331007 was minimal in human plasma. After a single 400 mg dose of [^14C]-sofosbuvir in healthy subjects, the blood to plasma ratio of ^14C-radioactivity was approximately 0.7.

Metabolism

In vitro, no detectable metabolism of ledipasvir was observed by human CYP1A2, CYP2C8, CYP2C9, CYP2C19, CYP2D6, and CYP3A4. Evidence of slow oxidative metabolism via an unknown mechanism has been observed. Following a single dose of 90 mg [^14C]-ledipasvir, systemic exposure was almost exclusively to the parent drug (greater than 98%). Unchanged ledipasvir is the major species present in feces.

Sofosbuvir is extensively metabolized in the liver to form the pharmacologically active nucleoside analog triphosphate GS-461203. The metabolic activation pathway involves sequential hydrolysis of the carboxyl ester moiety catalyzed by human cathepsin A (CatA) or carboxylesterase 1 (CES1) and phosphoramidate cleavage by histidine triad nucleotide-binding protein 1 (HINT1) followed by phosphorylation by the pyrimidine nucleotide biosynthesis pathway. Dephosphorylation results in the formation of nucleoside metabolite GS-331007 that cannot be efficiently rephosphorylated and lacks anti-HCV activity in vitro. After a single 400 mg oral dose of [^14C]-sofosbuvir, GS-331007 accounted for approximately greater than 90% of total systemic exposure.

Elimination

Following a single 90 mg oral dose of [^14C]-ledipasvir, mean total recovery of the [^14C]-radioactivity in feces and urine was approximately 87%, with most of the radioactive dose recovered from feces (approximately 86%). Unchanged ledipasvir excreted in feces accounted for a mean of 70% of the administered dose and the oxidative metabolite M19 accounted for 2.2% of the dose. These data indicate that biliary excretion of unchanged ledipasvir is a major route of elimination, with renal excretion being a minor pathway (approximately 1%). The median terminal half-life of ledipasvir following administration of HARVONI was 47 hours.

Following a single 400 mg oral dose of [^14C]-sofosbuvir, mean total recovery of the dose was greater than 92%, consisting of approximately 80%, 14%, and 2.5% recovered in urine, feces, and expired air, respectively. The majority of the sofosbuvir dose recovered in urine was GS-331007 (78%) while 3.5% was recovered as sofosbuvir. These data indicate that renal clearance is the major elimination pathway for GS-331007. The median terminal half-lives of sofosbuvir and GS-331007 following administration of HARVONI were 0.5 and 27 hours, respectively.

Specific Populations

Race: Population pharmacokinetics analysis in HCV-infected subjects indicated that race had no clinically relevant effect on the exposure of ledipasvir, sofosbuvir, and GS-331007.

Gender: Population pharmacokinetics analysis in HCV-infected subjects indicated that gender had no clinically relevant effect on the exposure of sofosbuvir and GS-331007. AUC and Cmax of ledipasvir were 77% and 58% higher, respectively, in females than males; however, the relationship between gender and ledipasvir exposures was not considered clinically relevant, as high response rates (SVR12 >90%) were achieved in male and female subjects across the Phase 3 studies and the safety profiles are similar in females and males.

Pediatric Patients: The pharmacokinetics of ledipasvir, sofosbuvir, and GS-331007 were determined in HCV genotype 1, 3, or 4 infected pediatric subjects 3 years of age and older receiving a daily dose of HARVONI as described below in Table 7. Exposures in pediatric subjects were similar to those observed in adults.

Table 7 Pharmacokinetic Properties of the Components of HARVONI in HCV-Infected Pediatric Subjects 3 Years of Age and Older [Population PK derived parameters]
Weight Group | Dose | PK Parameter | Geometric Mean (%CV)
Weight Group | Dose | PK Parameter | Ledipasvir | Sofosbuvir | GS-331007
≥35 kg [Ledipasvir N=100; Sofosbuvir N=72; GS-331007 N=100] | 90/400 mg | AUCtau (ng∙hr/mL) | 11200 (45.7) | 1350 (45.2) | 13600 (18.9)
≥35 kg [Ledipasvir N=100; Sofosbuvir N=72; GS-331007 N=100] | 90/400 mg | Cmax (ng/mL) | 550 (44.2) | 660 (51.1) | 921 (17.8)
17 to <35 kg [Ledipasvir N=86; Sofosbuvir N=66; GS-331007 N=86] | 45/200 mg | AUCtau (ng∙hr/mL) | 8750 (46.6) | 1420 (34.2) | 10700 (30.9)
17 to <35 kg [Ledipasvir N=86; Sofosbuvir N=66; GS-331007 N=86] | 45/200 mg | Cmax (ng/mL) | 440 (42.7) | 690 (24.8) | 958 (26.1)
<17 kg [Ledipasvir N=9; Sofosbuvir N=9; GS-331007 N=9] | 33.75/150 mg | AUCtau (ng∙hr/mL) | 7460 (31.0) | 1720 (23.2) | 12200 (15.2)
<17 kg [Ledipasvir N=9; Sofosbuvir N=9; GS-331007 N=9] | 33.75/150 mg | Cmax (ng/mL) | 405 (25.7) | 791 (16.6) | 1070 (13.0)

The pharmacokinetics of ledipasvir, sofosbuvir, and GS-331007 have not been established in pediatric subjects less than 3 years of age [see Use in Specific Populations (8.4) and Clinical Studies (14.7)].

Geriatric Patients: Population pharmacokinetic analysis in HCV-infected subjects showed that within the age range (18 to 80 years) analyzed, age did not have a clinically relevant effect on the exposure to ledipasvir, sofosbuvir, and GS-331007 [see Use in Specific Populations (8.5)].

Patients with Renal Impairment: The pharmacokinetics of ledipasvir were studied with a single dose of 90 mg ledipasvir in HCV negative subjects with severe renal impairment (eGFR less than 30 mL/min by Cockcroft-Gault). No clinically relevant differences in ledipasvir pharmacokinetics were observed between healthy subjects and subjects with severe renal impairment.

The pharmacokinetics of sofosbuvir were studied in HCV negative subjects with mild (eGFR between 50 to less than 80 mL/min/1.73 m^2), moderate (eGFR between 30 to less than 50 mL/min/1.73 m^2), severe renal impairment (eGFR less than 30 mL/min/1.73 m^2), and subjects with ESRD requiring hemodialysis following a single 400 mg dose of sofosbuvir. Relative to subjects with normal renal function (eGFR greater than 80 mL/min/1.73 m^2), the sofosbuvir AUC0–inf was 61%, 107%, and 171% higher in mild, moderate, and severe renal impairment, while the GS-331007 AUC0–inf was 55%, 88%, and 451% higher, respectively. In subjects with ESRD, relative to subjects with normal renal function, sofosbuvir and GS-331007 AUC0–inf was 28% and 1280% higher when sofosbuvir was dosed 1 hour before hemodialysis compared with 60% and 2070% higher when sofosbuvir was dosed 1 hour after hemodialysis, respectively. A 4-hour hemodialysis session removed approximately 18% of administered dose [see Dosage and Administration (2.6) and Use in Specific Populations (8.6)].

The pharmacokinetics of ledipasvir, sofosbuvir, and GS-331007 were studied in HCV-infected subjects with severe renal impairment or ESRD requiring dialysis treated with HARVONI for 8, 12, or 24 weeks. The results were generally consistent with those observed in HCV-negative subjects with ESRD requiring dialysis.

Patients with Hepatic Impairment: The pharmacokinetics of ledipasvir were studied with a single dose of 90 mg ledipasvir in HCV negative subjects with severe hepatic impairment (Child-Pugh Class C). Ledipasvir plasma exposure (AUC0–inf) was similar in subjects with severe hepatic impairment and control subjects with normal hepatic function. Population pharmacokinetics analysis in HCV-infected subjects indicated that cirrhosis (including decompensated cirrhosis) had no clinically relevant effect on the exposure of ledipasvir [see Use in Specific Populations (8.7)].

The pharmacokinetics of sofosbuvir were studied following 7-day dosing of 400 mg sofosbuvir in HCV-infected subjects with moderate and severe hepatic impairment (Child-Pugh Class B and C). Relative to subjects with normal hepatic function, the sofosbuvir AUC0–24 were 126% and 143% higher in moderate and severe hepatic impairment, while the GS-331007 AUC0–24 were 18% and 9% higher, respectively. Population pharmacokinetics analysis in HCV-infected subjects indicated that cirrhosis (including decompensated cirrhosis) had no clinically relevant effect on the exposure of sofosbuvir and GS-331007 [see Use in Specific Populations (8.7) and Clinical Studies (14.5)].

Drug Interaction Studies

Ledipasvir and sofosbuvir are substrates of drug transporters P-gp and BCRP while GS-331007 is not. P-gp inducers (e.g., rifampin or St. John's wort) may decrease ledipasvir and sofosbuvir plasma concentrations, leading to reduced therapeutic effect of HARVONI, and the use with P-gp inducers is not recommended with HARVONI [see Warnings and Precautions (5.3)]. Coadministration with drugs that inhibit P-gp and/or BCRP may increase ledipasvir and sofosbuvir plasma concentrations without increasing GS-331007 plasma concentration; HARVONI may be coadministered with P-gp and/or BCRP inhibitors. Neither ledipasvir nor sofosbuvir is a substrate for hepatic uptake transporters OCT1, OATP1B1, or OATP1B3. GS-331007 is not a substrate for renal transporters, including organic anion transporter OAT1 or OAT3, or organic cation transporter OCT2.

Ledipasvir is subject to slow oxidative metabolism via an unknown mechanism. In vitro, no detectable metabolism of ledipasvir by CYP enzymes has been observed. Biliary excretion of unchanged ledipasvir is a major route of elimination. Sofosbuvir is not a substrate for CYP and UGT1A1 enzymes. Clinically significant drug interactions with HARVONI mediated by CYP or UGT1A1 enzymes are not expected.

The effects of coadministered drugs on the exposure of ledipasvir, sofosbuvir, and GS-331007 are shown in Table 8 [see Drug Interactions (7)].

Table 8 Drug Interactions: Changes in Pharmacokinetic Parameters for Ledipasvir, Sofosbuvir, and the Predominant Circulating Metabolite GS-331007 in the Presence of the Coadministered Drug [All interaction studies conducted in healthy volunteers.]
Coadministered Drug | Dose of Coadministered Drug (mg) | Ledipasvir Dose (mg) | Sofosbuvir Dose (mg) | N | Mean Ratio (90% CI) of Ledipasvir, Sofosbuvir, and GS-331007 PK With/Without Coadministered Drug No Effect=1.00
Coadministered Drug | Dose of Coadministered Drug (mg) | Ledipasvir Dose (mg) | Sofosbuvir Dose (mg) | N |  | Cmax | AUC | Cmin
Atazanavir/ ritonavir + emtricitabine/ tenofovir DF [Data generated from simultaneous dosing with HARVONI. Staggered administration (12 hours apart) of atazanavir/ritonavir + emtricitabine/tenofovir DF or darunavir/ritonavir + emtricitabine/tenofovir DF and HARVONI provided similar results.] , [The effects of atazanavir/ritonavir on ledipasvir and sofosbuvir are similar with or without the presence of emtricitabine/tenofovir DF.] | 300/100 + 200/300 once daily | 90 once daily | 400 once daily | 24 | ledipasvir | 1.68 (1.54, 1.84) | 1.96 (1.74, 2.21) | 2.18 (1.91, 2.50)
Atazanavir/ ritonavir + emtricitabine/ tenofovir DF [Data generated from simultaneous dosing with HARVONI. Staggered administration (12 hours apart) of atazanavir/ritonavir + emtricitabine/tenofovir DF or darunavir/ritonavir + emtricitabine/tenofovir DF and HARVONI provided similar results.] , [The effects of atazanavir/ritonavir on ledipasvir and sofosbuvir are similar with or without the presence of emtricitabine/tenofovir DF.] | 300/100 + 200/300 once daily | 90 once daily | 400 once daily | 24 | sofosbuvir | 1.01 (0.88, 1.15) | 1.11 (1.02, 1.21) | NA
Atazanavir/ ritonavir + emtricitabine/ tenofovir DF [Data generated from simultaneous dosing with HARVONI. Staggered administration (12 hours apart) of atazanavir/ritonavir + emtricitabine/tenofovir DF or darunavir/ritonavir + emtricitabine/tenofovir DF and HARVONI provided similar results.] , [The effects of atazanavir/ritonavir on ledipasvir and sofosbuvir are similar with or without the presence of emtricitabine/tenofovir DF.] | 300/100 + 200/300 once daily | 90 once daily | 400 once daily | 24 | GS-331007 | 1.17 (1.12, 1.23) | 1.31 (1.25, 1.36) | 1.42 (1.34, 1.49)
Carbamazepine | 300 twice daily | ND | 400 single dose | 24 | sofosbuvir | 0.52 (0.43, 0.62) | 0.52 (0.46, 0.59) | NA
 | 300 twice daily | ND | 400 single dose | 24 | GS-331007 | 1.04 (0.97, 1.11) | 0.99 (0.94, 1.04) | NA
Cyclosporine | 600 single dose | ND | 400 single dose | 19 | sofosbuvir | 2.54 (1.87, 3.45) | 4.53 (3.26, 6.30) | NA
Cyclosporine | 600 single dose | ND | 400 single dose | 19 | GS-331007 | 0.60 (0.53, 0.69) | 1.04 (0.90, 1.20) | NA
Darunavir/ ritonavir | 800/100 once daily | 90 once daily | ND | 23 | ledipasvir | 1.45 (1.34, 1.56) | 1.39 (1.28, 1.49) | 1.39 (1.29, 1.51)
Darunavir/ ritonavir | 800/100 once daily | ND | 400 single dose | 18 | sofosbuvir | 1.45 (1.10, 1.92) | 1.34 (1.12, 1.59) | NA
Darunavir/ ritonavir | 800/100 once daily | ND | 400 single dose | 18 | GS-331007 | 0.97 (0.90, 1.05) | 1.24 (1.18, 1.30) | NA
Darunavir/ ritonavir + emtricitabine/ tenofovir DF | 800/100 + 200/300 once daily | 90 once daily | 400 once daily | 23 | ledipasvir | 1.11 (0.99, 1.24) | 1.12 (1.00, 1.25) | 1.17 (1.04, 1.31)
Darunavir/ ritonavir + emtricitabine/ tenofovir DF | 800/100 + 200/300 once daily | 90 once daily | 400 once daily | 23 | sofosbuvir | 0.63 (0.52, 0.75) | 0.73 (0.65, 0.82) | NA
Darunavir/ ritonavir + emtricitabine/ tenofovir DF | 800/100 + 200/300 once daily | 90 once daily | 400 once daily | 23 | GS-331007 | 1.10 (1.04, 1.16) | 1.20 (1.16, 1.24) | 1.26 (1.20, 1.32)
Efavirenz/ emtricitabine/ tenofovir DF [Administered as ATRIPLA® (efavirenz, emtricitabine, tenofovir DF).] | 600/200/300 once daily | 90 once daily | 400 once daily | 14 | ledipasvir | 0.66 (0.59, 0.75) | 0.66 (0.59, 0.75) | 0.66 (0.57, 0.76)
Efavirenz/ emtricitabine/ tenofovir DF [Administered as ATRIPLA® (efavirenz, emtricitabine, tenofovir DF).] | 600/200/300 once daily | 90 once daily | 400 once daily | 14 | sofosbuvir | 1.03 (0.87, 1.23) | 0.94 (0.81, 1.10) | NA
Efavirenz/ emtricitabine/ tenofovir DF [Administered as ATRIPLA® (efavirenz, emtricitabine, tenofovir DF).] | 600/200/300 once daily | 90 once daily | 400 once daily | 14 | GS-331007 | 0.86 (0.76, 0.96) | 0.90 (0.83, 0.97) | 1.07 (1.02, 1.13)
Elvitegravir/ cobicistat/ emtricitabine/ tenofovir alafenamide | 150/150/200/10 once daily | 90 once daily | 400 once daily | 30 | ledipasvir | 1.65 (1.53, 1.78) | 1.79 (1.64, 1.96) | 1.93 (1.74, 2.15)
Elvitegravir/ cobicistat/ emtricitabine/ tenofovir alafenamide | 150/150/200/10 once daily | 90 once daily | 400 once daily | 30 | sofosbuvir | 1.28 (1.13, 1.47) | 1.47 (1.35,1.59) | NA
Elvitegravir/ cobicistat/ emtricitabine/ tenofovir alafenamide | 150/150/200/10 once daily | 90 once daily | 400 once daily | 30 | GS-331007 | 1.29 (1.24, 1.35) | 1.48 (1.44, 1.53) | 1.66 (1.60, 1.73)
Famotidine | 40 single dose simultaneously with HARVONI | 90 single dose | 400 single dose | 12 | ledipasvir | 0.80 (0.69, 0.93) | 0.89 (0.76, 1.06) | NA
Famotidine | 40 single dose simultaneously with HARVONI | 90 single dose | 400 single dose | 12 | sofosbuvir | 1.15 (0.88, 1.50) | 1.11 (1.00, 1.24) | NA
Famotidine | 40 single dose simultaneously with HARVONI | 90 single dose | 400 single dose | 12 | GS-331007 | 1.06 (0.97, 1.14) | 1.06 (1.02, 1.11) | NA
Famotidine | 40 single dose 12 hours prior to HARVONI | 90 single dose | 400 single dose | 12 | ledipasvir | 0.83 (0.69, 1.00) | 0.98 (0.80, 1.20) | NA
Famotidine | 40 single dose 12 hours prior to HARVONI | 90 single dose | 400 single dose | 12 | sofosbuvir | 1.00 (0.76, 1.32) | 0.95 (0.82, 1.10) | NA
Famotidine | 40 single dose 12 hours prior to HARVONI | 90 single dose | 400 single dose | 12 | GS-331007 | 1.13 (1.07, 1.20) | 1.06 (1.01, 1.12) | NA
Methadone | 30 to 130 daily | ND | 400 once daily | 14 | sofosbuvir | 0.95 (0.68, 1.33) | 1.30 (1.00, 1.69) | NA
Methadone | 30 to 130 daily | ND | 400 once daily | 14 | GS-331007 | 0.73 (0.65, 0.83) | 1.04 (0.89, 1.22) | NA
Omeprazole | 20 once daily simultaneously with HARVONI | 90 single dose | 400 single dose | 16 | ledipasvir | 0.89 (0.61, 1.30) | 0.96 (0.66, 1.39) | NA
Omeprazole | 20 once daily simultaneously with HARVONI | 90 single dose | 400 single dose | 16 | sofosbuvir | 1.12 (0.88, 1.42) | 1.00 (0.80, 1.25) | NA
Omeprazole | 20 once daily simultaneously with HARVONI | 90 single dose | 400 single dose | 16 | GS-331007 | 1.14 (1.01, 1.29) | 1.03 (0.96, 1.12) | NA
Omeprazole | 20 once daily 2 hours prior to ledipasvir | 30 single dose | ND | 17 | ledipasvir | 0.52 (0.41, 0.66) | 0.58 (0.48, 0.71) | NA
Rifabutin | 300 once daily | ND | 400 single dose | 20 | sofosbuvir | 0.64 (0.53, 0.77) | 0.76 (0.63, 0.91) | NA
Rifabutin | 300 once daily | ND | 400 single dose | 20 | GS-331007 | 1.15 (1.03, 1.27) | 1.03 (0.95, 1.12) | NA
Rifampin | 600 once daily | 90 single dose [This study was conducted in the presence of two other investigational HCV direct-acting agents.] | ND | 31 | ledipasvir | 0.65 (0.56, 0.76) | 0.41 (0.36, 0.48) | NA
Rifampin | 600 once daily | ND | 400 single dose | 17 | sofosbuvir | 0.23 (0.19, 0.29) | 0.28 (0.24, 0.32) | NA
Rifampin | 600 once daily | ND | 400 single dose | 17 | GS-331007 | 1.23 (1.14, 1.34) | 0.95 (0.88, 1.03) | NA
Simeprevir | 150 once daily | 30 once daily | ND | 22 | ledipasvir | 1.81 (1.69, 2.94) | 1.92 (1.77, 2.07) | NA
Tacrolimus | 5 single dose | ND | 400 single dose | 16 | sofosbuvir | 0.97 (0.65, 1.43) | 1.13 (0.81, 1.57) | NA
Tacrolimus | 5 single dose | ND | 400 single dose | 16 | GS-331007 | 0.97 (0.83, 1.14) | 1.00 (0.87, 1.13) | NA
NA = not available/not applicable, ND = not dosed.
tenofovir DF = tenofovir disoproxil fumarate

No effect on the pharmacokinetic parameters of ledipasvir, sofosbuvir, and GS-331007 was observed with raltegravir and the combination of abacavir and lamivudine; emtricitabine, rilpivirine, and tenofovir disoproxil fumarate; or dolutegravir, emtricitabine, and tenofovir disoproxil fumarate.

Ledipasvir is an inhibitor of drug transporter P-gp and breast cancer resistance protein (BCRP) and may increase intestinal absorption of coadministered substrates for these transporters. Ledipasvir is an inhibitor of transporters OATP1B1, OATP1B3, and BSEP only at concentrations exceeding those achieved in clinic. Ledipasvir is not an inhibitor of transporters MRP2, MRP4, OCT2, OAT1, OAT3, MATE1, and OCT1. The drug-drug interaction potential of ledipasvir is primarily limited to the intestinal inhibition of P-gp and BCRP. Clinically relevant transporter inhibition by ledipasvir in the systemic circulation is not expected due to its high protein binding. Sofosbuvir and GS-331007 are not inhibitors of drug transporters P-gp, BCRP, MRP2, BSEP, OATP1B1, OATP1B3, and OCT1, and GS-331007 is not an inhibitor of OAT1, OCT2, and MATE1.

Ledipasvir, sofosbuvir, and GS-331007 are not inhibitors or inducers of CYP or UGT1A1 enzymes.

The effects of ledipasvir or sofosbuvir on the exposure of coadministered drugs are shown in Table 9 [see Drug Interactions (7)].

Table 9 Drug Interactions: Changes in Pharmacokinetic Parameters for Coadministered Drug in the Presence of Ledipasvir, Sofosbuvir, or HARVONI [All interaction studies conducted in healthy volunteers.]
Coadministered Drug | Dose of Coadministered Drug (mg) | Ledipasvir Dose (mg) | Sofosbuvir Dose (mg) | N | Mean Ratio (90% CI) of Coadministered Drug PK With/Without Ledipasvir, Sofosbuvir, or HARVONI No Effect=1.00
Coadministered Drug | Dose of Coadministered Drug (mg) | Ledipasvir Dose (mg) | Sofosbuvir Dose (mg) | N | Cmax | AUC | Cmin
Atazanavir/ ritonavir + emtricitabine /tenofovir DF [Data generated from simultaneous dosing with HARVONI. Staggered administration (12 hours apart) of atazanavir/ritonavir + emtricitabine/tenofovir DF or darunavir/ritonavir + emtricitabine/tenofovir DF and HARVONI provided similar results.] , [The effects of HARVONI on atazanavir and ritonavir are similar with or without the presence of emtricitabine/tenofovir DF.] , [This magnitude of change in tenofovir exposure does not reflect the approximately 60–80% increase caused by the effects of an HIV PI/ritonavir and the effect of food. Therefore, tenofovir exposure is approximately 130% higher when administered as tenofovir DF + atazanavir/ritonavir + HARVONI or tenofovir DF + darunavir/ritonavir + HARVONI and with food as compared to the tenofovir exposure observed following fasted administration of tenofovir DF-based regimens that do not contain an HIV PI/ritonavir and HARVONI.] | atazanavir 300 once daily | 90 once daily | 400 once daily | 24 | 1.07 (0.99, 1.14) | 1.27 (1.18, 1.37) | 1.63 (1.45, 1.84)
Atazanavir/ ritonavir + emtricitabine /tenofovir DF [Data generated from simultaneous dosing with HARVONI. Staggered administration (12 hours apart) of atazanavir/ritonavir + emtricitabine/tenofovir DF or darunavir/ritonavir + emtricitabine/tenofovir DF and HARVONI provided similar results.] , [The effects of HARVONI on atazanavir and ritonavir are similar with or without the presence of emtricitabine/tenofovir DF.] , [This magnitude of change in tenofovir exposure does not reflect the approximately 60–80% increase caused by the effects of an HIV PI/ritonavir and the effect of food. Therefore, tenofovir exposure is approximately 130% higher when administered as tenofovir DF + atazanavir/ritonavir + HARVONI or tenofovir DF + darunavir/ritonavir + HARVONI and with food as compared to the tenofovir exposure observed following fasted administration of tenofovir DF-based regimens that do not contain an HIV PI/ritonavir and HARVONI.] | ritonavir 100 once daily | 90 once daily | 400 once daily | 24 | 0.86 (0.79, 0.93) | 0.97 (0.89, 1.05) | 1.45 (1.27, 1.64)
Atazanavir/ ritonavir + emtricitabine /tenofovir DF [Data generated from simultaneous dosing with HARVONI. Staggered administration (12 hours apart) of atazanavir/ritonavir + emtricitabine/tenofovir DF or darunavir/ritonavir + emtricitabine/tenofovir DF and HARVONI provided similar results.] , [The effects of HARVONI on atazanavir and ritonavir are similar with or without the presence of emtricitabine/tenofovir DF.] , [This magnitude of change in tenofovir exposure does not reflect the approximately 60–80% increase caused by the effects of an HIV PI/ritonavir and the effect of food. Therefore, tenofovir exposure is approximately 130% higher when administered as tenofovir DF + atazanavir/ritonavir + HARVONI or tenofovir DF + darunavir/ritonavir + HARVONI and with food as compared to the tenofovir exposure observed following fasted administration of tenofovir DF-based regimens that do not contain an HIV PI/ritonavir and HARVONI.] | tenofovir DF 300 once daily | 90 once daily | 400 once daily | 24 | 1.47 (1.37, 1.58) | 1.35 (1.29, 1.42) | 1.47 (1.38, 1.57)
Darunavir/ ritonavir + emtricitabine/ tenofovir DF, | darunavir 800 once daily | 90 once daily | 400 once daily | 23 | 1.01 (0.96, 1.06) | 1.04 (0.99, 1.08) | 1.08 (0.98, 1.20)
Darunavir/ ritonavir + emtricitabine/ tenofovir DF, | ritonavir 100 once daily | 90 once daily | 400 once daily | 23 | 1.17 (1.01, 1.35) | 1.25 (1.15, 1.36) | 1.48 (1.34, 1.63)
Darunavir/ ritonavir + emtricitabine/ tenofovir DF, | tenofovir DF 300 once daily | 90 once daily | 400 once daily | 23 | 1.64 (1.54, 1.74) | 1.50 (1.42, 1.59) | 1.59 (1.49, 1.70)
Elvitegravir/ cobicistat/ emtricitabine/ tenofovir alafenamide | elvitegravir 150 once daily | 90 once daily | 400 once daily | 30 | 0.98 (0.90, 1.07) | 1.11 (1.02, 1.20) | 1.46 (1.28, 1.66)
Elvitegravir/ cobicistat/ emtricitabine/ tenofovir alafenamide | cobicistat 150 once daily | 90 once daily | 400 once daily | 30 | 1.23 (1.15, 1.32) | 1.53 (1.45, 1.62) | 3.25 (2.88, 3.67)
Elvitegravir/ cobicistat/ emtricitabine/ tenofovir alafenamide | tenofovir alafenamide 10 once daily | 90 once daily | 400 once daily | 30 | 0.90 (0.73, 1.11) | 0.86 (0.78, 0.95) | NA
Norelgestromin | norgestimate 0.180/0.215/0.25/ethinyl estradiol 0.025 once daily | 90 once daily | ND | 15 | 1.02 (0.89, 1.16) | 1.03 (0.90, 1.18) | 1.09 (0.91, 1.31)
Norelgestromin | norgestimate 0.180/0.215/0.25/ethinyl estradiol 0.025 once daily | ND | 400 once daily | 15 | 1.07 (0.94, 1.22) | 1.06 (0.92, 1.21) | 1.07 (0.89, 1.28)
Norgestrel | norgestimate 0.180/0.215/0.25/ethinyl estradiol 0.025 once daily | 90 once daily | ND | 15 | 1.03 (0.87, 1.23) | 0.99 (0.82, 1.20) | 1.00 (0.81, 1.23)
Norgestrel | norgestimate 0.180/0.215/0.25/ethinyl estradiol 0.025 once daily | ND | 400 once daily | 15 | 1.18 (0.99, 1.41) | 1.19 (0.98, 1.45) | 1.23 (1.00, 1.51)
Ethinyl estradiol | norgestimate 0.180/0.215/0.25/ethinyl estradiol 0.025 once daily | 90 once daily | ND | 15 | 1.40 (1.18, 1.66) | 1.20 (1.04, 1.39) | 0.98 (0.79, 1.22)
Ethinyl estradiol | norgestimate 0.180/0.215/0.25/ethinyl estradiol 0.025 once daily | ND | 400 once daily | 15 | 1.15 (0.97, 1.36) | 1.09 (0.94, 1.26) | 0.99 (0.80, 1.23)
Midazolam | 2.5 single dose | 90 single dose | ND | 30 | 1.07 (1.00, 1.14) | 0.99 (0.95, 1.04) | NA
Midazolam | 2.5 single dose | 90 single dose | ND | 30 | 0.95 (0.87, 1.04) | 0.89 (0.84, 0.95) | NA
Raltegravir | 400 twice daily | 90 once daily | ND | 28 | 0.82 (0.66, 1.02) | 0.85 (0.70, 1.02) | 1.15 (0.90, 1.46)
Raltegravir | 400 twice daily | ND | 400 single dose | 19 | 0.57 (0.44, 0.75) | 0.73 (0.59, 0.91) | 0.95 (0.81, 1.12)
Simeprevir | 150 once daily | 30 once daily | ND | 22 | 2.61 (2.39, 2.86) | 2.69 (2.44, 2.96) | NA
Tacrolimus | 5 single dose | ND | 400 single dose | 16 | 0.73 (0.59, 0.90) | 1.09 (0.84, 1.40) | NA
Tenofovir DF | 300 once daily [Administered as ATRIPLA (efavirenz, emtricitabine, tenofovir DF). The effects of HARVONI on tenofovir exposures are similar when tenofovir is administered as ATRIPLA, COMPLERA, or TRUVADA + dolutegravir.] | 90 once daily | 400 once daily | 15 | 1.79 (1.56, 2.04) | 1.98 (1.77, 2.23) | 2.63 (2.32, 2.97)
NA = not available/not applicable, ND = not dosed.
tenofovir DF = tenofovir disoproxil fumarate

No effect on the pharmacokinetic parameters of the following coadministered drugs was observed with ledipasvir or sofosbuvir: abacavir, cyclosporine, darunavir/ritonavir, dolutegravir, efavirenz, emtricitabine, lamivudine, methadone, or rilpivirine.

12.4 Microbiology

Mechanism of Action

Ledipasvir is an inhibitor of the HCV NS5A protein, which is required for viral replication. Resistance selection in cell culture and cross-resistance studies indicate ledipasvir targets NS5A as its mode of action.

Sofosbuvir is an inhibitor of the HCV NS5B RNA-dependent RNA polymerase, which is required for viral replication. Sofosbuvir is a nucleotide prodrug that undergoes intracellular metabolism to form the pharmacologically active uridine analog triphosphate (GS-461203), which can be incorporated into HCV RNA by the NS5B polymerase and acts as a chain terminator. In a biochemical assay, GS-461203 inhibited the polymerase activity of the recombinant NS5B from HCV genotypes 1b and 4a with IC50 values of 3.3 and 2.7 microM, respectively. GS-461203 is neither an inhibitor of human DNA and RNA polymerases nor an inhibitor of mitochondrial RNA polymerase.

Antiviral Activity

In HCV replicon assays, the EC50 values of ledipasvir against full-length replicons from genotypes 1a and 1b were 0.031 nM and 0.004 nM, respectively. The median EC50 values of ledipasvir against chimeric replicons encoding NS5A sequences from clinical isolates from treatment-naïve HCV-infected subjects were 0. 02 nM for genotype 1a (range 0.007–1.0 nM; N=23) and 0.006 nM for genotype 1b (range 0.002–1.0 nM; N=34). Ledipasvir had median EC50 values ranging between 0.002 nM to 0.16 nM against 11 genotype 4 subtypes (4a, 4d, 4n, 4r, 4o, 4c, 4f, 4k, 4l, 4m, and 4t). The median EC50 value for subtype 4b was 199.6 nM (range 0.66–1799 nM; N=3); the two 4b isolates with EC50 values greater than 100 nM had NS5A resistance-associated polymorphisms L30S+M31M+P58S+Y93H. The median EC50 value of ledipasvir was 0.03 nM against genotype 5a isolates (range 0.008–0.081 nM; N=35). For genotype 6, the EC50 values for ledipasvir varied by subtype. Subtypes 6a and 6h had median EC50 values of 0.55 and 0.17 nM, respectively. For subtypes 6e, 6l, 6n, 6q, 6k, and 6m, the median EC50 values ranged from 60.6 nM to 430.1 nM.

In HCV replicon assays, the EC50 values of sofosbuvir against full-length replicons from genotypes 1a, 1b, and 4a, and chimeric 1b replicons encoding NS5B from genotypes 5a or 6a ranged from 14–110 nM. The median EC50 value of sofosbuvir against chimeric replicons encoding NS5B sequences from clinical isolates was 62 nM for genotype 1a (range 29–128 nM; N=67) and 102 nM for genotype 1b (range 45–170 nM; N=29). In replication competent virus assays, the EC50 value of sofosbuvir against genotype 1a was 30 nM. Evaluation of sofosbuvir in combination with ledipasvir showed no antagonistic effect in reducing HCV RNA levels in replicon cells.

Resistance

In Cell Culture

HCV replicons with reduced susceptibility to ledipasvir have been selected in cell culture for genotypes 1a and 1b. Reduced susceptibility to ledipasvir was associated with the primary NS5A amino acid substitution Y93H in both genotypes 1a and 1b. Additionally, a Q30E substitution emerged in genotype 1a replicons. Site-directed mutagenesis of the Y93H in both genotypes 1a and 1b, as well as the Q30E substitution in genotype 1a, conferred high levels of reduced susceptibility to ledipasvir (fold change in EC50 greater than 1000-fold).

HCV replicons with reduced susceptibility to sofosbuvir have been selected in cell culture for multiple genotypes including 1b, 4a, 5a, and 6a. Reduced susceptibility to sofosbuvir was associated with the NS5B substitution S282T in all replicon genotypes examined. An M289L substitution developed along with the S282T substitution in genotype 5 and 6 replicons. Site-directed mutagenesis of the S282T substitution in replicons of 8 genotypes conferred 2- to 18-fold reduced susceptibility to sofosbuvir.

In Clinical Trials

Genotype 1

In a pooled analysis of subjects who received HARVONI in Phase 3 trials (ION-3, ION-1, and ION-2), 37 subjects (29 with genotype 1a HCV and 8 with genotype 1b HCV) qualified for resistance analysis due to virologic failure (35 with virologic relapse, 2 with breakthrough on-treatment due to documented non-adherence). Post-baseline NS5A and NS5B deep nucleotide sequence analysis data (assay sensitivity of 1%) were available for 37/37 and 36/37 subjects' viruses, respectively.

Of the 29 genotype 1a virologic failure subjects, 55% (16/29) of subjects had virus with emergent NS5A resistance-associated substitutions K24R, M28T/V, Q30R/H/K/L, L31M, or Y93H/N at failure. Five of these 16 subjects' viruses also had baseline NS5A polymorphisms at resistance-associated amino acid positions. The most common substitutions detected at failure were Q30R, Y93H or N, and L31M.

Of the 8 genotype 1b virologic failure subjects, 88% (7/8) had virus with emergent NS5A resistance-associated substitutions L31V/M/I or Y93H at failure. Virus from three of these 7 subjects also had baseline NS5A polymorphisms at resistance-associated positions. The most common substitution detected at failure was Y93H.

At failure, 38% (14/37) of virologic failure subjects' viruses had 2 or more NS5A substitutions at resistance-associated positions.

In the SOLAR-1 and SOLAR-2 trials (liver transplant recipients or subjects with decompensated liver disease), there were 24 virologic failures with genotype 1 infection (20 relapsers and 4 subjects who discontinued treatment prior to achieving HCV RNA <LLOQ). Treatment-emergent NS5A resistance-associated substitutions K24R, M28T, Q30R/H/K, L31V, H58D/P, and/or Y93H/C were detected in 14/17 (82%) genotype 1a virologic failure subjects, and R30Q, L31M, and/or Y93H/N were detected in 6/7 (86%) genotype 1b virologic failure subjects.

In phenotypic analyses, post-baseline isolates from subjects who harbored NS5A resistance-associated substitutions at failure showed 20- to >243-fold reduced susceptibility to ledipasvir.

Treatment-emergent NS5B substitutions L159 (n=1) and V321 (n=2) previously associated with sofosbuvir failure were detected in the Phase 3 trials (ION-3, ION-1, and ION-2). In addition, treatment-emergent NS5B substitutions at highly conserved positions D61G (n=3), A112T (n=2), E237G (n=2), and S473T (n=1) were detected at low frequency by next generation sequencing in treatment failure subjects infected with HCV genotype 1a. The D61G substitution was previously described in subjects infected with HCV genotype 1a in a liver pre-transplant trial. The E237G substitution was detected in 3 subjects infected with HCV GT1a in the SOLAR-1 and SOLAR-2 trials. The clinical significance of these substitutions is currently unknown. The sofosbuvir-associated resistance substitution S282T in NS5B was not detected in any failure isolate from the Phase 3 trials. NS5B substitutions S282T, L320V/I, and V321I in combination with NS5A substitutions L31M, Y93H, and Q30L were detected in one subject at failure following 8 weeks of treatment with HARVONI in a Phase 2 trial.

Genotype 4, 5 or 6

Resistance analysis was performed for 6 relapse subjects infected with HCV genotype 4 (Study 1119 and ION-4, N=3), genotype 5 (Study 1119, N=2) or genotype 6 (ELECTRON-2, N=1) and treated with HARVONI for 12 weeks. All the relapse subjects with NS5A sequencing data (5 of 6) had pretreatment NS5A resistance-associated polymorphisms (single or combinations at positions 24, 28, 30, 31, and 58). NS5A resistance substitutions (Y93C or L28V) emerged in two of the genotype 4 relapse subjects post-treatment who also had NS5A polymorphisms pretreatment that were retained post-treatment. Two of the relapsers with genotype 4 HCV infection had an NS5B V321I substitution pretreatment, which was retained post-treatment. Three of the relapse subjects (1 each for genotype 4, 5, and 6) had virus with emergent sofosbuvir resistance-associated substitution S282T at relapse; the genotype 5 relapse subject also had emergent nucleotide inhibitor substitution M289I.

Persistence of Resistance-Associated Substitutions

Certain NS5A inhibitor resistance-associated substitutions have been found to persist for >1 year in some patients. The long-term clinical impact of the emergence or persistence of virus containing ledipasvir or sofosbuvir resistance-associated substitutions is unknown.

Effect of Baseline HCV Polymorphisms on Treatment Response

Adults

Genotype 1

Analyses were conducted to explore the association between pre-existing baseline NS5A polymorphisms at resistance-associated positions and relapse rates. In the pooled analysis of the Phase 3 trials, 23% (370/1589) of subjects' virus had baseline NS5A polymorphisms at resistance-associated positions (any change from reference at NS5A amino acid positions 24, 28, 30, 31, 58, 92, or 93) identified by population or analysis of deep nucleotide sequences with a 15% frequency threshold.

In treatment-naïve subjects whose virus had baseline NS5A polymorphisms at resistance-associated positions in Studies ION-1 and ION-3, relapse rates were 6% (3/48) after 8 weeks and 1% (1/113) after 12 weeks of treatment with HARVONI. Relapse rates among subjects without baseline NS5A polymorphisms at resistance-associated positions were 5% (8/167) after 8 weeks and 1% (3/306) after 12 weeks of treatment with HARVONI.

In treatment-experienced subjects in Study ION-2 whose virus had baseline NS5A polymorphisms at resistance-associated positions, relapse rates were 22% (5/23) after 12 weeks and 0% (0/19) after 24 weeks of treatment with HARVONI. In another study in treatment-experienced subjects (SIRIUS), 0/15 (0%) subjects with NS5A polymorphisms at resistance-associated positions relapsed after 12 weeks of treatment with HARVONI + ribavirin compared to 2/15 (13%) subjects treated with 24 weeks of HARVONI.

SVR was achieved in all 24 subjects (N=20 with L159F+C316N; N=1 with L159F; and N=3 with N142T) who had baseline polymorphisms associated with resistance to sofosbuvir and/or other NS5B nucleoside inhibitors. The NS5B S282T substitution associated with resistance to sofosbuvir was not detected in the baseline NS5B sequence of any subject in Phase 3 trials by population or deep nucleotide sequence analysis.

In the SOLAR-1 and SOLAR-2 trials (liver transplant recipients or subjects with decompensated liver disease), after 12 weeks of treatment with HARVONI and ribavirin, relapse rates were 7% (5/71) and 5% (10/217) in genotype 1 subjects with and without baseline NS5A polymorphisms at resistance-associated positions, respectively.

In the Phase 3 trials and SOLAR trials, the specific baseline NS5A resistance-associated polymorphisms observed among subjects who relapsed were M28T/V, Q30H/R, L31M, H58D/P, and Y93H/N in genotype 1a, and L28M, L31M, A92T, and Y93H in genotype 1b. Subjects with multiple NS5A polymorphisms at resistance-associated positions appeared to have higher relapse rates.

Genotype 4, 5 or 6

Phylogenetic analysis of HCV sequences from genotype 4-infected subjects in Study 1119 (N=44) and ION-4 (N=8) identified 7 HCV genotype 4 subtypes (4a, 4b, 4d, 4f, 4m, 4o, and 4r). Most subjects were infected with subtype 4a (N=32; 62%) or 4d (N=11; 21%); 1 to 3 subjects were infected with each of the other genotype 4 subtypes. There were 3 subjects with subtype 4r, 2 of whom experienced virologic relapse, and both had a combination of 2 pretreatment NS5A resistance-associated polymorphisms (L28M/V+L30R).

Phylogenetic analysis of HCV sequences from genotype 5-infected subjects in Study 1119 showed almost all were subtype 5a (N=39) with one subject not having a subtype identified at screening or by analysis.

Phylogenetic analysis of HCV sequences from genotype 6-infected subjects in ELECTRON-2 identified 7 HCV genotype 6 subtypes (6a, 6e, 6l, 6m, 6p, 6q, and 6r). Thirty-two percent of the subjects had subtype 6a and 24% had subtype 6e. One to three subjects were infected with the other subtypes 6l, 6m, 6p, 6q, or 6r. The one subject who did not achieve SVR12 had subtype 6l.

Although the data are limited, baseline HCV NS5A resistance-associated polymorphisms are not expected to impact the likelihood of achieving SVR when HARVONI is used as recommended to treat HCV genotype 4, 5, or 6-infected patients, based on the low virologic failure rate observed in Study 1119 and ELECTRON-2. The specific baseline polymorphisms observed in subjects with virologic failure were L28M/V, L30R, and P58T for genotype 4; L31M for genotype 5; and Q24K, F28V, R30A, and T58P for genotype 6.

Relapse occurred in 2 of 3 genotype 4 subjects who had baseline NS5B V321I, a polymorphism at a position associated with treatment failure to sofosbuvir and other nucleoside inhibitors; these two subjects also had baseline NS5A resistance-associated polymorphisms. For genotype 5 and 6, SVR12 was achieved in subjects who had baseline NS5B polymorphisms at positions associated with resistance to sofosbuvir and other nucleoside inhibitors (N=1 with N142T in genotype 5; N=1 with M289I in genotype 5; N=15 with M289L/I in genotype 6). The sofosbuvir resistance-associated substitution S282T was not detected in the baseline NS5B sequence of any subject with genotype 4, 5, or 6 HCV in clinical trials by population or deep nucleotide sequence analysis.

Pediatrics

In Study 1116, the presence of NS5A and NS5B resistance-associated polymorphisms did not impact treatment outcome; all pediatric subjects 3 years of age and older with baseline NS5A or NS5B nucleoside inhibitor resistance-associated polymorphisms (14%; 32/223) achieved SVR following 12 weeks treatment with HARVONI.

Cross Resistance

Based on resistance patterns observed in cell culture replicon studies and HCV-infected subjects, cross-resistance between ledipasvir and other NS5A inhibitors is expected. Both sofosbuvir and ledipasvir were fully active against substitutions associated with resistance to other classes of direct-acting antivirals with different mechanisms of action, such as NS5B non-nucleoside inhibitors and NS3 protease inhibitors. The efficacy of ledipasvir/sofosbuvir has not been established in patients who have previously failed treatment with other regimens that include an NS5A inhibitor.

13 NONCLINICAL TOXICOLOGY

13.1 Carcinogenesis, Mutagenesis, Impairment of Fertility

Carcinogenesis and Mutagenesis

Ledipasvir: Ledipasvir was not genotoxic in a battery of in vitro or in vivo assays, including bacterial mutagenicity, chromosome aberration using human peripheral blood lymphocytes, and in vivo rat micronucleus assays.

Ledipasvir was not carcinogenic in a 6-month rasH2 transgenic mouse study (up to 300 mg/kg/day). Similarly, ledipasvir was not carcinogenic in a 2-year rat study (up to 100 mg/kg/day in males and 30 mg/kg/day in females), resulting in exposures approximately 10 and 4 times, respectively, higher than the exposure in humans at the recommended human dose (RHD).

Sofosbuvir: Sofosbuvir was not genotoxic in a battery of in vitro or in vivo assays, including bacterial mutagenicity, chromosome aberration using human peripheral blood lymphocytes, and in vivo mouse micronucleus assays.

Sofosbuvir was not carcinogenic in a 2-year mouse study (up to 200 mg/kg/day in males and 600 mg/kg/day in females) and in a 2-year rat study (up to 750 mg/kg/day), resulting in exposures of the predominant circulating metabolite GS-331007 of approximately 4 and 18 times (in mice) and 8 and 10 times (in rats), in males and females respectively, the exposure in humans at the RHD.

Impairment of Fertility

Ledipasvir: Ledipasvir had no adverse effects on mating and fertility. In female rats, the mean number of corpora lutea and implantation sites were reduced slightly at maternal exposures approximately 3 times the exposure in humans at the RHD. At the highest dose levels without effects, exposures of ledipasvir were approximately 5 and 2 times, in males and females, respectively, the exposure in humans at the RHD.

Sofosbuvir: Sofosbuvir had no effects on embryo-fetal viability or on fertility when evaluated in rats. At the highest dose tested, exposure to the predominant circulating metabolite GS-331007 was approximately 5 times the exposure in humans at the RHD.

14 CLINICAL STUDIES

14.1 Description of Clinical Trials

The efficacy and safety of HARVONI were evaluated in four trials in genotype 1 HCV mono-infected subjects including one trial exclusively in treatment-experienced subjects with compensated cirrhosis (Child-Pugh A); one trial in genotype 1 or 4 HCV/HIV-1 coinfected subjects; two trials in genotype 4, 5, or 6 HCV mono-infected subjects; two trials in genotype 1 or 4 HCV infected pretransplant subjects with decompensated cirrhosis (Child-Pugh B and C) or post-transplant with Metavir F0–F3 fibrosis, compensated cirrhosis, decompensated cirrhosis, or fibrosing cholestatic hepatitis (FCH); two trials in subjects with severe renal impairment (one of which included subjects requiring dialysis); and one trial in genotype 1 or 4 HCV pediatric subjects 3 years of age and older without cirrhosis or with compensated cirrhosis, as summarized in Table 10 [see Clinical Studies (14.2, 14.3, 14.4, 14.5, 14.6, and 14.7)]:

Table 10 Trials Conducted with HARVONI with or without Ribavirin in Subjects with Chronic HCV Genotype 1, 4, 5, or 6 Infection
Trial | Population | Study Arms (Number of Subjects Treated)
ION-3 [Open-label.] (NCT01851330) | GT1, TN without cirrhosis | HARVONI 8 weeks (215) HARVONI + RBV 8 weeks (216) HARVONI 12 weeks (216)
ION-1 (NCT01701401) | GT1, TN with or without cirrhosis | HARVONI 12 weeks (214) HARVONI + RBV 12 weeks (217) HARVONI 24 weeks (217) HARVONI + RBV 24 weeks (217)
ION-2 (NCT01768286) | GT1, TE [TE = Treatment-experienced subjects including those who have failed a peginterferon alfa + RBV based regimen with or without an HCV protease inhibitor.] with or without cirrhosis | HARVONI 12 weeks (109) HARVONI + RBV 12 weeks (111) HARVONI 24 weeks (109) HARVONI + RBV 24 weeks (111)
SIRIUS [Double-blind, placebo-controlled.] (NCT01965535) | GT1, TE with cirrhosis | HARVONI + RBV 12 Weeks (77) HARVONI 24 weeks (77)
ION-4 (NCT02073656) | GT1 and GT4 HCV/HIV-1 coinfected TN and TE with or without cirrhosis | HARVONI 12 Weeks (N=327 for GT1; N=8 for GT4)
1119 (NCT02081079) | GT4 and GT5, TN and TE with or without cirrhosis | HARVONI 12 Weeks (N=44 for GT4; N=41 for GT5)
ELECTRON-2 (NCT01826981) | GT6, TN and TE with or without cirrhosis | HARVONI 12 Weeks (25)
SOLAR-1 and SOLAR-2 (NCT01938430 and NCT02010255) | GT1 and GT4 pre-transplant with decompensated cirrhosis or post-transplant with Metavir F0–F3 fibrosis, compensated cirrhosis, decompensated cirrhosis, or FCH | HARVONI + RBV 12 Weeks (336) HARVONI + RBV 24 weeks (334)
1116 (NCT02249182) | GT1 or 4 TN and TE with or without cirrhosis in pediatric subjects 3 years of age and older | HARVONI 12 Weeks (223) HARVONI 24 Weeks (1)
0154 (NCT01958281) | GT1 TN and TE with severe RI without dialysis | HARVONI 12 weeks (18)
4063 (NCT03036839) | GT1, 5, or 6 TN and TE [TE = Treatment experienced subjects including those who have failed either interferon/peginterferon alfa/ribavirin based regimens or HCV-specific direct-acting antiviral regimens that do not include an NS5A polymerase inhibitor.] with or without compensated cirrhosis, with ESRD requiring dialysis | HARVONI 8 Weeks (45) HARVONI 12 Weeks (12) HARVONI 24 Weeks (6)
ESRD = End stage renal disease; RBV = ribavirin; RI = Renal impairment; TN = Treatment-naïve subjects.

HARVONI was administered once daily by mouth in these trials. For subjects without cirrhosis or with compensated cirrhosis who received ribavirin, the ribavirin dosage was 1000 mg per day for subjects weighing less than 75 kg or 1200 mg per day for subjects weighing at least 75 kg. For subjects with decompensated cirrhosis in SOLAR-1 and SOLAR-2 studies, the starting ribavirin dosage was 600 mg per day regardless of transplantation status. Ribavirin dose adjustments were performed according to the ribavirin labeling.

Serum HCV RNA values were measured during the clinical trials using the COBAS TaqMan HCV test (version 2.0), for use with the High Pure System in ION-3, ION-1, ION-2, SIRIUS, and ION-4 studies or the COBAS AmpliPrep/COBAS Taqman HCV test (version 2.0) in ELECTRON-2, 1119, SOLAR-1, SOLAR-2, and 1116 studies. The COBAS TaqMan HCV test (version 2.0) for use with the High Pure System has a lower limit of quantification (LLOQ) of 25 IU per mL and the COBAS AmpliPrep/COBAS Taqman HCV test (version 2.0) has a LLOQ of 15 IU per mL. Sustained virologic response (SVR12), defined as HCV RNA less than LLOQ at 12 weeks after the cessation of treatment, was the primary endpoint in studies in adults and the key efficacy endpoint in the study in pediatric subjects 12 years of age and older. Relapse was a secondary endpoint, which was defined as HCV RNA greater than or equal to LLOQ with 2 consecutive values or last available post-treatment measurement during the post-treatment period after achieving HCV RNA less than LLOQ at end of treatment.

14.2 Clinical Trials in Subjects with Genotype 1 HCV

Treatment-Naïve Adults without Cirrhosis – ION-3 (Study 0108)

ION-3 was a randomized, open-label trial in treatment-naïve non-cirrhotic subjects with genotype 1 HCV. Subjects were randomized in a 1:1:1 ratio to one of the following three treatment groups and stratified by HCV genotype (1a vs 1b): HARVONI for 8 weeks, HARVONI for 12 weeks, or HARVONI + ribavirin for 8 weeks.

Demographics and baseline characteristics were balanced across the treatment groups. Of the 647 treated subjects, the median age was 55 years (range: 20 to 75); 58% of the subjects were male; 78% were White; 19% were Black; 6% were Hispanic or Latino; mean body mass index was 28 kg/m^2 (range: 18 to 56 kg/m^2); 81% had baseline HCV RNA levels greater than or equal to 800,000 IU per mL; 80% had genotype 1a HCV infection; 73% had non-C/C IL28B alleles (CT or TT).

Table 11 presents the SVR12 for the HARVONI treatment groups in the ION-3 trial after 8 and 12 weeks of HARVONI treatment. Ribavirin was not shown to increase the SVR12 observed with HARVONI. Therefore, the HARVONI + ribavirin arm is not presented in Table 11.

Table 11 Study ION-3: SVR12 after 8 and 12 Weeks of Treatment in Treatment-Naïve Non-Cirrhotic Subjects with Genotype 1 HCV
 | HARVONI 8 Weeks (N=215) | HARVONI 12 Weeks (N=216)
SVR12 | 94% (202/215) | 96% (208/216)
Outcome for Subjects without SVR
On-Treatment Virologic Failure | 0/215 | 0/216
Relapse [The denominator for relapse is the number of subjects with HCV RNA <LLOQ at their last on-treatment assessment.] | 5% (11/215) | 1% (3/216)
Other [Other includes subjects who did not achieve SVR and did not meet virologic failure criteria (e.g., lost to follow-up).] | 1% (2/215) | 2% (5/216)
SVR by Genotype [One subject without a confirmed subtype for genotype 1 infection was excluded from this subgroup analysis.]
Genotype 1a | 93% (159/171) | 96% (165/172)
Genotype 1b | 98% (42/43) | 98% (43/44)

The treatment difference between the 8-week treatment of HARVONI and 12-week treatment of HARVONI was −2.3% (97.5% confidence interval −7.2% to 2.5%). Among subjects with a baseline HCV RNA less than 6 million IU per mL, the SVR12 was 97% (119/123) with 8-week treatment of HARVONI and 96% (126/131) with 12-week treatment of HARVONI.

Relapse rates by baseline viral load are presented in Table 12.

Table 12 Study ION-3: Relapse Rates by Baseline Viral Load after 8 and 12 Weeks of Treatment in Treatment-Naïve Non-Cirrhotic Subjects with Genotype 1 HCV
 | HARVONI 8 Weeks (N=215) | HARVONI 12 Weeks (N=216)
Number of Responders at End of Treatment | 215 | 216
Baseline HCV RNA [HCV RNA values were determined using the Roche TaqMan Assay; a subject's HCV RNA may vary from visit to visit.]
HCV RNA <6 million IU/mL | 2% (2/123) | 2% (2/131)
HCV RNA ≥6 million IU/mL | 10% (9/92) | 1% (1/85)

Treatment-Naïve Adults with or without Cirrhosis – ION-1 (Study 0102)

ION-1 was a randomized, open-label trial that evaluated 12 and 24 weeks of treatment with HARVONI with or without ribavirin in 865 treatment-naïve subjects with genotype 1 HCV including those with cirrhosis. Subjects were randomized in a 1:1:1:1 ratio to receive HARVONI for 12 weeks, HARVONI + ribavirin for 12 weeks, HARVONI for 24 weeks, or HARVONI + ribavirin for 24 weeks. Randomization was stratified by the presence or absence of cirrhosis and HCV genotype (1a vs 1b).

Demographics and baseline characteristics were balanced across the treatment groups. Of the 865 treated subjects, the median age was 54 years (range: 18 to 80); 59% of the subjects were male; 85% were White; 12% were Black; 12% were Hispanic or Latino; mean body mass index was 27 kg/m^2 (range: 18 to 48 kg/m^2); 79% had baseline HCV RNA levels greater than or equal to 800,000 IU per mL; 67% had genotype 1a HCV infection; 70% had non-C/C IL28B alleles (CT or TT); and 16% had cirrhosis.

Table 13 presents the SVR12 for the treatment group of HARVONI for 12 weeks in the ION-1 trial. Ribavirin was not shown to increase SVR12 observed with HARVONI. Therefore, the HARVONI + ribavirin arm is not presented in Table 13.

Table 13 Study ION-1: SVR12 after 12 Weeks of Treatment in Treatment-Naïve Subjects with Genotype 1 HCV with and without Cirrhosis
 | HARVONI 12 Weeks (N=214)
SVR12 [Excluding one subject with genotype 4 infection.] | 99% (210/213)
Outcome for Subjects without SVR
On-Treatment Virologic Failure | 0/213
Relapse, [The denominator for relapse is the number of subjects with HCV RNA <LLOQ at their last on-treatment assessment.] | <1% (1/212)
Other, [Other includes subjects who did not achieve SVR12 and did not meet virologic failure criteria (e.g., lost to follow-up).] | 1% (2/213)

SVR12 for selected subgroups are presented in Table 14.

Table 14 Study ION-1: SVR12 for Selected Subgroups after 12 Weeks of Treatment in Treatment-Naïve Subjects with Genotype 1 HCV with and without Cirrhosis
 | HARVONI 12 Weeks (N=214)
Genotype [One subject without a confirmed subtype for genotype 1 infection and one subject with genotype 4 infection were excluded from this subgroup analysis.]
Genotype 1a | 98% (142/145)
Genotype 1b | 100% (67/67)
Cirrhosis [Subjects with missing cirrhosis status were excluded from this subgroup analysis.]
No | 99% (176/177)
Yes | 94% (32/34)

Previously-Treated Adults with or without Cirrhosis – ION-2 (Study 0109)

ION-2 was a randomized, open-label trial that evaluated 12 and 24 weeks of treatment with HARVONI with or without ribavirin in genotype 1 HCV-infected subjects with or without cirrhosis who failed prior therapy with an interferon-based regimen, including regimens containing an HCV protease inhibitor. Subjects were randomized in a 1:1:1:1 ratio to receive HARVONI for 12 weeks, HARVONI + ribavirin for 12 weeks, HARVONI for 24 weeks, or HARVONI + ribavirin for 24 weeks. Randomization was stratified by the presence or absence of cirrhosis, HCV genotype (1a vs 1b) and response to prior HCV therapy (relapse/breakthrough vs nonresponse).

Demographics and baseline characteristics were balanced across the treatment groups. Of the 440 treated subjects, the median age was 57 years (range: 24 to 75); 65% of the subjects were male; 81% were White; 18% were Black; 9% were Hispanic or Latino; mean body mass index was 28 kg/m^2 (range: 19 to 50 kg/m^2); 89% had baseline HCV RNA levels greater than or equal to 800,000 IU per mL; 79% had genotype 1a HCV infection; 88% had non-C/C IL28B alleles (CT or TT); and 20% had cirrhosis. Forty-seven percent (47%) of the subjects failed a prior therapy of pegylated interferon and ribavirin. Among these subjects, 49% were relapse/breakthrough and 51% were non-responder. Fifty-three percent (53%) of the subjects failed a prior therapy of pegylated interferon and ribavirin with an HCV protease inhibitor. Among these subjects, 62% were relapse/breakthrough and 38% were non-responder.

Table 15 presents the SVR12 for the HARVONI treatment groups in the ION-2 trial. Ribavirin was not shown to increase SVR12 observed with HARVONI. Therefore, the HARVONI + ribavirin arms are not presented in Table 15.

Table 15 Study ION-2: SVR12 after 12 and 24 Weeks of Treatment in Subjects with Genotype 1 HCV with or without Cirrhosis Who Failed Prior Therapy
 | HARVONI 12 Weeks (N=109) | HARVONI 24 Weeks (N=109)
SVR12 | 94% (102/109) | 99% (108/109)
Outcome for Subjects without SVR
On-Treatment Virologic Failure | 0/109 | 0/109
Relapse [The denominator for relapse is the number of subjects with HCV RNA <LLOQ at their last on-treatment assessment.] | 6% (7/108) | 0/109
Other [Other includes subjects who did not achieve SVR12 and did not meet virologic failure criteria (e.g., lost to follow-up).] | 0/109 | 1% (1/109)

Among the subjects with available SVR12 and SVR24 data (206/218), all subjects who achieved SVR12 in the ION-2 study also achieved SVR24.

SVR12 and relapse rates for selected subgroups are presented in Tables 16 and 17.

Table 16 Study ION-2: SVR12 for Selected Subgroups after 12 and 24 Weeks of Treatment in Subjects with Genotype 1 HCV Who Failed Prior Therapy
 | HARVONI 12 Weeks (N=109) | HARVONI 24 Weeks (N=109)
Genotype
Genotype 1a | 95% (82/86) | 99% (84/85)
Genotype 1b | 87% (20/23) | 100% (24/24)
Cirrhosis [Subjects with missing cirrhosis status were excluded from this subgroup analysis.]
No | 95% (83/87) | 99% (85/86)
Yes | 86% (19/22) | 100% (22/22)
Prior HCV Therapy
Peg-IFN + RBV | 93% (40/43) | 100% (58/58)
HCV protease inhibitor + Peg-IFN + RBV | 94% (62/66) | 98% (49/50)
Response to Prior HCV Therapy
Relapse/Breakthrough | 95% (57/60) | 100% (60/60)
Non-responder | 92% (45/49) | 98% (48/49)
RBV = ribavirin.

Table 17 Study ION-2: Relapse Rates for Selected Subgroups after 12 and 24 Weeks of Treatment in Subjects with Genotype 1 HCV Who Failed Prior Therapy
 | HARVONI 12 Weeks (N=109) | HARVONI 24 Weeks (N=109)
Number of Responders at End of Treatment | 108 | 109
Cirrhosis [Subjects with missing cirrhosis status were excluded from this subgroup analysis.]
No | 5% (4/86) [These 4 non-cirrhotic relapsers all had baseline NS5A resistance-associated polymorphisms.] | 0% (0/86)
Yes | 14% (3/22) | 0% (0/22)
Presence of Baseline NS5A Resistance-Associated Polymorphisms [NS5A resistance-associated polymorphisms include any change at NS5A positions 24, 28, 30, 31, 58, 92, or 93.]
No | 2% (2/85) | 0% (0/90)
Yes | 22% (5/23) | 0% (0/19)
IL28B Status
C/C | 0% (0/10) | 0% (0/16)
Non-C/C | 7% (7/98) | 0% (0/93)

Previously-Treated Adults with Cirrhosis – SIRIUS (Study 0121)

SIRIUS was a randomized, double-blind and placebo-controlled trial that evaluated the efficacy of HARVONI + ribavirin for 12 weeks or HARVONI without ribavirin for 24 weeks in genotype 1 HCV-infected subjects with compensated cirrhosis who failed prior therapy with a Peg-IFN + ribavirin regimen followed by a subsequent Peg-IFN + ribavirin + an HCV protease inhibitor regimen. Subjects were randomized in a 1:1 ratio to receive placebo for 12 weeks followed by HARVONI + ribavirin for 12 weeks or HARVONI for 24 weeks. Randomization was stratified by HCV genotype (1a vs 1b) and response to prior HCV therapy (never achieved HCV RNA less than LLOQ vs achieved HCV RNA less than LLOQ).

Demographics and baseline characteristics were balanced across the treatment groups. Of the 155 randomized subjects, the median age was 56 years (range: 23 to 77); 74% of the subjects were male; 97% were White; mean body mass index was 27 kg/m^2 (range: 19 to 47 kg/m^2); 63% had genotype 1a HCV infection; 94% had non-C/C IL28B alleles (CT or TT). One subject discontinued therapy while on placebo, and was not included in the efficacy analysis.

The SVR12 was 96% (74/77) and 97% (75/77) in subjects treated with HARVONI + ribavirin for 12 weeks and HARVONI for 24 weeks without ribavirin, respectively. All 5 subjects who did not achieve SVR12 relapsed.

14.3 Clinical Trials in Subjects with Genotype 4, 5, or 6 HCV

Below are trial descriptions, SVR12, and relapse data in the genotype 4, 5, and 6 HCV populations. Trial results in the genotype 4, 5, and 6 HCV populations are based upon limited number of subjects in some subgroups, particularly in subjects who have been previously treated and subjects with cirrhosis.

Genotype 4

In two open-label studies (Study 1119 and ION-4), HARVONI was administered for 12 weeks to treatment-naïve and previously-treated adult subjects with genotype 4 HCV infection. Study 1119 enrolled 44 treatment-naïve or previously-treated subjects with genotype 4 HCV, with or without cirrhosis. ION-4 enrolled 4 treatment-naïve and 4 previously-treated subjects with genotype 4 HCV infection who were coinfected with HIV-1, none of whom had cirrhosis.

In Study 1119, the overall SVR12 rate was 93% (41/44). SVR12 was similar based upon prior HCV treatment history and cirrhosis status. In ION-4, all 8 subjects achieved SVR12.

Genotype 5

In the open-label 1119 trial, HARVONI was administered for 12 weeks to 41 treatment-naïve or previously treated adult subjects with genotype 5 HCV infection, with or without cirrhosis. The overall SVR12 was 93% (38/41). SVR12 was similar based upon prior HCV treatment history and cirrhosis status.

Genotype 6

In the open-label ELECTRON-2 trial, HARVONI was administered for 12 weeks to 25 treatment-naïve or previously treated adult subjects with genotype 6 HCV infection, with or without cirrhosis. The overall SVR12 was 96% (24/25). SVR12 was similar based upon prior HCV treatment history and cirrhosis status. The single subject who relapsed discontinued study treatment early (at approximately Week 8).

14.4 Clinical Trials in Subjects Coinfected with HCV and HIV-1

ION-4 was an open-label clinical trial that evaluated the safety and efficacy of 12 weeks of treatment with HARVONI without ribavirin in HCV treatment-naïve and previously treated adult subjects with genotype 1 or 4 HCV infection who were coinfected with HIV-1. Treatment-experienced subjects had failed prior treatment with Peg-IFN + ribavirin, Peg-IFN + ribavirin + an HCV protease inhibitor, or sofosbuvir + ribavirin. Subjects were on a stable HIV-1 antiretroviral therapy that included emtricitabine + tenofovir disoproxil fumarate, administered with efavirenz, rilpivirine, or raltegravir.

Of the 335 treated subjects, the median age was 52 years (range: 26 to 72); 82% of the subjects were male; 61% were White; 34% were Black; mean body mass index was 27 kg/m^2 (range: 18 to 66 kg/m^2); 75% had genotype 1a HCV infection; 2% had genotype 4 infection; 76% had non-C/C IL28B alleles (CT or TT); and 20% had compensated cirrhosis. Fifty-five percent (55%) of the subjects were treatment-experienced.

Table 18 presents the SVR12 in the ION-4 trial after 12 weeks of HARVONI treatment.

Table 18 Study ION-4: SVR12 in Subjects with Genotype 1 or 4 HCV Coinfected with HIV-1
 | HARVONI 12 Weeks (N=335)
SVR12 | 96% (321/335)
Outcome for Subjects without SVR
On-Treatment Virologic Failure | <1% (2/335)
Relapse [The denominator for relapse is the number of subjects with HCV RNA <LLOQ at their last on-treatment assessment.] | 3% (10/333)
Other [Other includes subjects who did not achieve SVR12 and did not meet virologic failure criteria (e.g., lost to follow-up).] | <1% (2/335)

SVR12 rates were 94% (63/67) in subjects with cirrhosis and 98% (46/47) in subjects who were previously treated and had cirrhosis. The relapse rate in the ION-4 trial in Black subjects was 9% (10/115), all of whom were IL28B non-CC genotype, and none in non-Black subjects (0/220). In the ION-1, ION-2, and ION-3 HCV mono-infection studies, relapse rates were 3% (10/305) in Black subjects and 2% (26/1637) in non-Black subjects.

No subject had HIV-1 rebound during the study. The percentage of CD4+ cells did not change during treatment. Median CD4+ cell count increase of 29 cells/mm^3 was observed at the end of treatment with HARVONI for 12 weeks.

14.5 Clinical Trials in Liver Transplant Recipients and/or Subjects with Decompensated Cirrhosis

SOLAR-1 and SOLAR-2 were two open-label trials that evaluated 12 and 24 weeks of treatment with HARVONI in combination with ribavirin in HCV treatment-naïve and previously treated adult subjects with genotype 1 and 4 infection who had undergone liver transplantation and/or who had decompensated liver disease. The two trials were identical in study design. Subjects were enrolled in one of the seven groups in the trials based on liver transplantation status and severity of hepatic impairment (see Table 19). Subjects with a CPT score greater than 12 were excluded. Within each group, subjects were randomized in a 1:1 ratio to receive HARVONI + ribavirin for 12 weeks or HARVONI + ribavirin for 24 weeks. For subjects with decompensated cirrhosis in SOLAR-1 and SOLAR-2 studies, the starting ribavirin dosage was 600 mg per day regardless of transplantation status. Ribavirin dose adjustments were performed according to the ribavirin labeling [see Clinical Studies (14.1)].

Demographics and baseline characteristics were balanced across the treatment groups. Of the 670 treated subjects, the median age was 59 years (range: 21 to 81); 77% of the subjects were male; 91% were White; mean body mass index was 28 kg/m^2 (range: 18 to 49 kg/m^2); 94% and 6% had genotype 1 and 4 HCV infection, respectively; 78% of the subjects failed a prior HCV therapy.

Table 19 presents the pooled SVR12 rates for SOLAR-1 and SOLAR-2 in subjects with genotype 1 HCV treated with HARVONI + ribavirin for 12 weeks. The SVR12 rates observed with 24 weeks of HARVONI + ribavirin were similar to the SVR12 rates observed with 12 weeks of treatment. Therefore, the results for the HARVONI + ribavirin 24 weeks arm are not presented in Table 19.

Table 19 Studies SOLAR-1 and SOLAR-2: SVR12 and Relapse Rates After 12 Weeks of Treatment with HARVONI and Ribavirin in Subjects with Genotype 1 HCV Who Were Post Liver Transplant and/or Who Had Decompensated Liver Disease
 | HARVONI + RBV 12 weeks (N=307)
 | SVR12 (N=300) [Five subjects transplanted prior to post-treatment Week 12 with HCV RNA<LLOQ at last measurement prior to transplant were excluded.] , [Two subjects were excluded due to failure to meet the inclusion criteria for any of the treatment groups (i.e., did not have decompensated cirrhosis and had also not received a liver transplant).] | Relapse (N=288),, [Twelve subjects were excluded from relapse analysis because they died (N=11) or withdrew consent (N=1) prior to reaching the 12-week post-treatment follow-up visit.]
Pre-transplant
CPT B | 87% (45/52) | 12% (6/51)
CPT C | 88% (35/40) | 5% (2/37)
Post-transplant
Metavir score F0–F3 | 95% (94/99) | 3% (3/97)
CPT A | 98% (55/56) | 0% (0/55)
CPT B | 89% (41/46) | 2% (1/42)
CPT C | 57% (4/7) | 33% (2/6)

There were 7 subjects with fibrosing cholestatic hepatitis in the 12-week treatment arm, and all subjects achieved SVR12.

In genotype 4 HCV post-transplant subjects without cirrhosis or with compensated cirrhosis treated with HARVONI + ribavirin for 12 weeks (N=12), the SVR12 rate was similar to rates reported with genotype 1; no subjects relapsed. Available data in subjects with genotype 4 HCV who had decompensated cirrhosis (pre- and post-liver transplantation) were insufficient for dosing recommendations; therefore, these results are not presented.

14.6 Clinical Trials in Adults with Severe Renal Impairment, Including those Requiring Dialysis

Trial 0154 was an open-label clinical trial that evaluated 12 weeks of treatment with HARVONI in 18 treatment-naïve and treatment-experienced (subjects with prior exposure to an HCV NS5B polymerase inhibitor were excluded) genotype 1 HCV-infected adults with severe renal impairment not requiring dialysis. At baseline, two subjects (11%) had cirrhosis and the mean eGFR was 24.9 mL/min (range: 9.0 to 39.6). The SVR rate was 100% (18/18).

As shown in the table below, Trial 4063 was an open-label three-arm clinical trial that evaluated 8, 12, and 24 weeks of treatment with HARVONI in a total of 63 adults with chronic HCV infection and ESRD requiring dialysis. Of the 63 subjects, 10% had cirrhosis, 24% were treatment-experienced, 95% were on hemodialysis, and 5% were on peritoneal dialysis; mean duration on dialysis was 12 years (range: 0.2 to 43 years). The SVR rates for the 8, 12, and 24 week HARVONI treatment groups are shown in Table 20.

Table 20 Trial 4063: SVR12 after 8, 12, and 24 Weeks of Treatment in Adults with HCV with or without Cirrhosis and with Severe Renal Impairment Requiring Dialysis
 | HARVONI 8 Weeks (N=45) | HARVONI 12 Weeks (N=12) | HARVONI 24 Weeks (N=6)
Population | Treatment-naïve, GT 1 HCV Non-cirrhotic | Treatment-naïve and treatment- experienced [Subjects with prior exposure to any HCV NS5A inhibitor were excluded.] GT 1, 5, 6 [One subject had an indeterminant HCV GT.] HCV Non-cirrhotic | Treatment-experienced, GT 1 HCV with compensated cirrhosis
SVR12 | 93% (42/45) | 100% (12/12) | 83% (5/6)
Outcome for Subjects without SVR
On-Treatment Virologic Failure | 0/45 | 0/12 | 0/6
Relapse | 0/44 | 0/12 | 0/6
Other ["Other" outcomes includes subjects who did not achieve SVR and did not meet virologic failure criteria. All subjects who failed without virologic relapse or on-treatment virologic failure died prior to follow-up Week 12. None of these deaths were assessed as treatment-related.] | 7% (3/45) | 0/12 | 17% (1/6)

14.7 Clinical Trial in Pediatric Subjects

The efficacy of HARVONI was evaluated in an open-label trial (Study 1116) in 224 HCV treatment-naïve (N=186) and treatment-experienced (N=38) pediatric subjects 3 years of age or older. This study evaluated 12 weeks of treatment with HARVONI once daily in genotype 1 (N=183) or genotype 4 (N=3) treatment-naive subjects without cirrhosis or with compensated cirrhosis; genotype 1 treatment-experienced subjects without cirrhosis (N=37); and evaluated 24 weeks of treatment with HARVONI once daily in one genotype 1 subject who was both treatment-experienced and cirrhotic.

Subjects 12 Years to <18 Years of Age: HARVONI was evaluated in 100 subjects 12 years to <18 years of age with HCV genotype 1 infection. Demographics and baseline characteristics were balanced across treatment-naïve and treatment-experienced subjects (patients had failed an interferon based regimen with or without ribavirin). The median age was 15 years (range: 12 to 17); 63% of the subjects were female; 91% were White, 7% were Black, and 2% were Asian; 13% were Hispanic/Latino; mean body mass index was 23 kg/m^2 (range: 13.1 to 36.6 kg/m^2); mean weight was 61 kg (range 33 to 126 kg); 55% had baseline HCV RNA levels greater than or equal to 800,000 IU/mL; 81% had genotype 1a HCV infection. One subject (treatment-naïve) had known compensated cirrhosis. The majority of subjects (84%) had been infected through vertical transmission.

The SVR12 rate was 98% overall (98% [78/80] in treatment-naïve subjects and 100% [20/20] in treatment-experienced subjects). No subject experienced on-treatment virologic failure or relapse. Two subjects were lost to follow-up.

Subjects 6 Years to <12 Years of Age: HARVONI was evaluated in 90 subjects 6 years to <12 years of age with HCV genotype 1 or 4 infection. Among these subjects, 72 (80%) were treatment-naïve and 18 (20%) were treatment-experienced. Eighty-nine of the subjects (87 with genotype 1 HCV infection and 2 with genotype 4 HCV infection) were treated with HARVONI for 12 weeks, 1 subject with genotype 1 HCV infection was treated with HARVONI for 24 weeks. The median age was 9 years (range: 6 to 11); 59% of the subjects were male; 79% were White, 8% were Black, and 6% were Asian; 10% were Hispanic/Latino; mean body mass index was 18 kg/m^2 (range: 13 to 31kg/m^2); mean weight was 33 kg (range 18 to 76 kg); 59% had baseline HCV RNA levels greater than or equal to 800,000 IU/mL; 86% had genotype 1a HCV infection; 2 subjects (1 treatment-naïve, 1 treatment-experienced) had known compensated cirrhosis. The majority of subjects (97%) had been infected through vertical transmission.

The SVR12 rate was 99% (86/87) in subjects with genotype 1 HCV infection, and 100% (2/2) in subjects with genotype 4 HCV infection. The one genotype 1 subject treated with HARVONI for 24 weeks also achieved SVR12. The one subject (genotype 1) who did not achieve SVR12 and relapsed had been treated with HARVONI for 12 weeks.

Subjects 3 Years to <6 Years of Age: HARVONI was evaluated in 34 subjects 3 years to <6 years of age with HCV genotype 1 (N = 33) or genotype 4 (N = 1) infection. All of the subjects were treatment-naïve and treated with HARVONI for 12 weeks. The median age was 5 years (range: 3 to 5); 71% of the subjects were female; 79% were White, 3% were Black, and 6% were Asian; 18% were Hispanic/Latino; mean body mass index was 17 kg/m^2 (range: 13 to 25 kg/m^2); mean weight was 19 kg (range 11 to 34 kg); 56% had baseline HCV RNA levels greater than or equal to 800,000 IU/mL; 82% had genotype 1a HCV infection; no subjects had known cirrhosis. All subjects (100%) had been infected through vertical transmission.

The SVR12 rate was 97% (32/33) in subjects with genotype 1 HCV infection, and the one subject with genotype 4 HCV infection also achieved SVR12. One subject prematurely discontinued study treatment due to an adverse event.

16 HOW SUPPLIED/STORAGE AND HANDLING

STORAGE AND HANDLING

Tablets

HARVONI tablets 90 mg/400 mg are orange, diamond-shaped, film-coated, debossed with "GSI" on one side and "7985" on the other side of the tablet. Each bottle contains 28 tablets (NDC 61958-1801-1), a silica gel desiccant and polyester coil, and is closed with a child-resistant closure.

HARVONI tablets, 45 mg/200 mg, are white, capsule-shaped, film-coated, debossed with "GSI" on one side and "HRV" on the other side of the tablet. Each bottle contains 28 tablets (NDC 61958-1803-1), a silica gel desiccant and polyester coil, and is closed with a child-resistant closure.

- Store below 30 °C (86 °F).
- Dispense only in original container.
- Do not use if seal over bottle opening is broken or missing.

STORAGE AND HANDLING

Oral Pellets

HARVONI pellets, 45 mg/200 mg, are orange pellets supplied as unit-dose packets in cartons. Each carton contains 28 packets (NDC 61958-1804-1).

HARVONI pellets, 33.75 mg/150 mg, are orange pellets supplied as unit-dose packets in cartons. Each carton contains 28 packets (NDC 61958-1805-1).

- Store below 30 °C (86 °F).
- Do not use if carton tamper-evident seal or packet seal is broken or damaged.

17 PATIENT COUNSELING INFORMATION

Advise the patient to read the FDA-approved patient labeling (Patient Information and Instructions for Use).

Risk of Hepatitis B Virus Reactivation in Patients Coinfected with HCV and HBV

Inform patients that HBV reactivation can occur in patients coinfected with HBV during or after treatment of HCV infection. Advise patients to tell their healthcare provider if they have a history of HBV infection [see Warnings and Precautions (5.1)].

Serious Symptomatic Bradycardia When Coadministered with Amiodarone

Advise patients to seek medical evaluation immediately for symptoms of bradycardia such as near-fainting or fainting, dizziness or lightheadedness, malaise, weakness, excessive tiredness, shortness of breath, chest pain, confusion, or memory problems [see Warnings and Precautions (5.2), Adverse Reactions (6.2), and Drug Interactions (7.2)].

Drug Interactions

Inform patients that HARVONI may interact with other drugs. Advise patients to report to their healthcare provider the use of any other prescription or nonprescription medication or herbal products including St. John's wort [see Warnings and Precautions (5.2, 5.3) and Drug Interactions (7)].

Pregnancy

Advise patients to avoid pregnancy during combination treatment with HARVONI and ribavirin and for 6 months after completion of treatment. Inform patients to notify their healthcare provider immediately in the event of a pregnancy [see Use in Specific Populations (8.1)].

Hepatitis C Virus Transmission

Inform patients that the effect of treatment of hepatitis C infection on transmission is not known, and that appropriate precautions to prevent transmission of the hepatitis C virus during treatment or in the event of treatment failure should be taken.

Administration

Advise patients to take HARVONI every day at the regularly scheduled time with or without food. Inform patients that it is important not to miss or skip doses and to take HARVONI for the duration that is recommended by the physician.

For HARVONI oral pellets, advise patients or caregivers to read and follow the Instructions for Use for preparing the correct dose.

Manufactured and distributed by:
Gilead Sciences, Inc.
Foster City, CA 94404

HARVONI, ATRIPLA, COMPLERA, TRUVADA and VIREAD are trademarks of Gilead Sciences, Inc., or its related companies. All other trademarks referenced herein are the property of their respective owners.

© 2024 Gilead Sciences, Inc. All rights reserved.
205834-GS-012

Patient Information

HARVONI® (har-VOE-nee)
(ledipasvir and sofosbuvir)
tablets

HARVONI® (har-VOE-nee)
(ledipasvir and sofosbuvir)
oral pellets

Important: If you take HARVONI with ribavirin, you should also read the Medication Guide for ribavirin.

What is the most important information I should know about HARVONI?

HARVONI can cause serious side effects, including,
Hepatitis B virus reactivation: Before starting treatment with HARVONI, your healthcare provider will do blood tests to check for hepatitis B virus infection. If you have ever had hepatitis B virus infection, the hepatitis B virus could become active again during or after treatment of hepatitis C virus with HARVONI. Hepatitis B virus becoming active again (called reactivation) may cause serious liver problems including liver failure and death. Your healthcare provider will monitor you if you are at risk for hepatitis B virus reactivation during treatment and after you stop taking HARVONI.

For more information about side effects, see the section "What are the possible side effects of HARVONI?"

What is HARVONI?

HARVONI is a prescription medicine used to treat adults and children 3 years of age and older with chronic (lasting a long time) hepatitis C virus (HCV):

- genotype 1, 4, 5, or 6 infection without cirrhosis or with compensated cirrhosis
- genotype 1 infection with advanced cirrhosis (decompensated) in combination with ribavirin
- genotype 1 or 4 infection without cirrhosis or with compensated cirrhosis who have had a liver transplant, in combination with ribavirin

It is not known if HARVONI is safe and effective in children with HCV under 3 years of age.

Before taking HARVONI, tell your healthcare provider about all of your medical conditions, including if you:

- have ever had hepatitis B virus infection
- have liver problems other than hepatitis C infection
- have had a liver transplant
- have kidney problems or you are on dialysis
- have HIV infection
- are pregnant or plan to become pregnant. It is not known if HARVONI will harm your unborn baby.
  - Males and females who take HARVONI in combination with ribavirin should also read the ribavirin Medication Guide for important pregnancy, contraception, and infertility information.
- are breastfeeding or plan to breastfeed. It is not known if HARVONI passes into your breast milk.
  - Talk to your healthcare provider about the best way to feed your baby during treatment with HARVONI.

Tell your healthcare provider about all of the medicines you take, including prescription and over-the-counter medicines, vitamins, and herbal supplements. HARVONI and other medicines may affect each other. This can cause you to have too much or not enough HARVONI or other medicines in your body. This may affect the way HARVONI or your other medicines work, or may cause side effects. Keep a list of your medicines to show your healthcare provider and pharmacist.

- You can ask your healthcare provider or pharmacist for a list of medicines that interact with HARVONI.

Do not start taking a new medicine without telling your healthcare provider. Your healthcare provider can tell you if it is safe to take HARVONI with other medicines.

How should I take HARVONI?

- Take HARVONI exactly as your healthcare provider tells you to take it. Do not change your dose unless your healthcare provider tells you to.
- Do not stop taking HARVONI without first talking with your healthcare provider.
- Take HARVONI tablets or oral pellets by mouth, with or without food.
- It is important that you do not miss or skip doses of HARVONI during treatment.
- For adults the usual dose of HARVONI is one 90/400 mg tablet each day.
- For children 3 years of age and older your healthcare provider will prescribe the right dose of HARVONI tablets or oral pellets based on your child's body weight.
  - Tell your healthcare provider if your child has problems with swallowing tablets.
  - If your healthcare provider prescribes HARVONI oral pellets for your child, see "How should I give HARVONI oral pellets to my child."
- Do not miss a dose of HARVONI. Missing a dose lowers the amount of medicine in your blood. Refill your HARVONI prescription before you run out of medicine.

If you take too much HARVONI, call your healthcare provider or go to the nearest hospital emergency room right away.

How should I give HARVONI oral pellets to my child?
See the detailed Instructions for Use for information about how to give or take a dose of HARVONI oral pellets.

- Administer HARVONI oral pellets exactly as instructed by your healthcare provider.
- Do not open the packet until ready to use.
- Hold the HARVONI pellets packet with the cut line on top.
- Shake the HARVONI pellets packet gently to settle the pellets.
- Tear or cut the HARVONI packet along the cut line.
- HARVONI oral pellets can be taken right in the mouth without chewing, or with food.
- If HARVONI pellets are taken with food, sprinkle the pellets on one or more spoonfuls of non-acidic soft food at or below room temperature. Examples of non-acidic foods include pudding, chocolate syrup, mashed potato, and ice cream. Take HARVONI pellets within 30 minutes of gently mixing with food and swallow the entire contents without chewing to avoid a bitter taste.
- Do not store any leftover HARVONI mixture (oral pellets mixed with food) for use at a later time. Throw away any unused portion.

What are the possible side effects of HARVONI?

HARVONI can cause serious side effects, including:

- Hepatitis B virus reactivation. See "What is the most important information I should know about HARVONI?"
- Slow heart rate (bradycardia). HARVONI treatment may result in slowing of the heart rate along with other symptoms when taken with amiodarone (Cordarone®, Nexterone®, Pacerone®), a medicine used to treat certain heart problems. In some cases bradycardia has led to death or the need for a heart pacemaker when amiodarone is taken with HARVONI. Get medical help right away if you take amiodarone with HARVONI and get any of the following symptoms:

- fainting or near-fainting
- dizziness or lightheadedness
- not feeling well

- weakness
- extreme tiredness
- shortness of breath

- chest pains
- confusion
- memory problems

The most common side effects of HARVONI include:

- tiredness

- headache

- weakness

These are not all the possible side effects of HARVONI. For more information, ask your healthcare provider or pharmacist.

Call your doctor for medical advice about side effects. You may report side effects to FDA at 1-800-FDA-1088.

How should I store HARVONI?

- Store HARVONI tablets or pellets below 86°F (30°C).
- Keep HARVONI tablets in the original container.
- Do not use HARVONI tablets if the seal over the bottle opening is broken or missing.
- Do not use HARVONI pellets if the carton tamper-evident seal, or the pellets packet seal, is broken or damaged.

Keep HARVONI and all medicines out of the reach of children.

General information about the safe and effective use of HARVONI

Medicines are sometimes prescribed for purposes other than those listed in a Patient Information leaflet. Do not use HARVONI for a condition for which it was not prescribed. Do not give HARVONI to other people, even if they have the same symptoms you have. It may harm them.

You can ask your healthcare provider or pharmacist for information about HARVONI that is written for health professionals.

What are the ingredients in HARVONI?

Active ingredients: ledipasvir and sofosbuvir

Inactive ingredients, Tablets 90/400 mg: colloidal silicon dioxide, copovidone, croscarmellose sodium, lactose monohydrate, magnesium stearate, and microcrystalline cellulose.

The tablet film-coat contains: FD&C yellow #6/sunset yellow FCF aluminum lake, polyethylene glycol, polyvinyl alcohol, talc, and titanium dioxide.

Inactive ingredients, Tablets 45/200 mg: colloidal silicon dioxide, copovidone, croscarmellose sodium, lactose monohydrate, magnesium stearate, and microcrystalline cellulose.

The tablet film-coat contains: polyethylene glycol, polyvinyl alcohol partially hydrolyzed, talc, and titanium dioxide.

Inactive ingredients, Oral Pellets: amino-methacrylate copolymer, colloidal silicon dioxide, copovidone, croscarmellose sodium, hypromellose, iron oxide red, iron oxide yellow, lactose monohydrate, magnesium stearate, microcrystalline cellulose, polyethylene glycol, talc, and titanium dioxide.

Manufactured and distributed by:
Gilead Sciences, Inc., Foster City, CA 94404
For more information, call 1-800-445-3235 or go to www.HARVONI.com.
HARVONI is a trademark of Gilead Sciences, Inc. All other trademarks referenced herein are the property of their respective owners.
©2024 Gilead Sciences, Inc. All rights reserved.
205834-GS-012

This Patient Information has been approved by the U.S. Food and Drug Administration

Revised: 03/2020

INSTRUCTIONS FOR USE HARVONI® (har-VOE-nee) (ledipasvir and sofosbuvir) pellets, for oral use

Read the Patient Information that comes with HARVONI oral pellets for important information about HARVONI.

This Instructions for Use contains information on how to take HARVONI oral pellets. Be sure you understand and follow the instructions. If you have any questions, ask your healthcare provider or pharmacist.

Important Information You Need to Know Before Taking HARVONI oral pellets

- For oral use only (take by mouth with or without food).
- Do not open the HARVONI oral pellet packet(s) until ready to use.
- HARVONI oral pellets are orange pellets supplied as single-use packets in cartons. Each carton contains 28 packets.
- Do not use HARVONI oral pellets if the carton tamper-evident seal, or the pellets packet seal, is broken or damaged.

Preparing a dose of HARVONI oral pellets to be taken with food:

Before you prepare a dose of HARVONI oral pellets to be taken with food, gather the following supplies:

- Daily HARVONI oral pellet packet(s), as prescribed by your healthcare provider
- One or more spoonfuls of non-acidic soft food such as pudding, chocolate syrup, mashed potato, or ice cream
- Bowl
- Spoon
- Scissors (optional)

Step 1: Add one or more spoonfuls of non-acidic soft food to the bowl first.

Step 2: Hold the HARVONI oral pellets packet with the cut line on top (see Figure A).

Step 3: Shake the packet gently to settle the pellets to the bottom of the packet (see Figure B).

Figure A

Figure B

Step 4: Cut the packet along the cut line with scissors (see Figure C), or fold the packet back at the tear line (see Figure D) and tear open (see Figure E).

Figure C

Figure D

Figure E

Step 5: Carefully pour the entire contents of the prescribed number of HARVONI oral pellet packet(s) onto the food in the bowl and gently mix with a spoon (see Figure F). Make sure that no HARVONI oral pellets remain in the packet(s).

Figure F

Step 6: Take the HARVONI oral pellets and food mixture within 30 minutes without chewing to avoid a bitter taste. Ensure all of the HARVONI oral pellets are taken.

Preparing a dose of HARVONI oral pellets to be taken without food:

Before you prepare a dose of HARVONI oral pellets to be taken without food, gather the following supplies:

- Daily HARVONI oral pellet packet(s), as prescribed by your healthcare provider
- Scissors (optional)
- Water (optional)

Step 1: Hold the HARVONI oral pellets packet with the cut line on top (see Figure G).

Step 2: Shake the packet gently to settle the pellets to the bottom of the packet (see Figure H).

Figure G

Figure H

Step 3: Cut the packet along the cut line with scissors (see Figure I), or fold the packet back at the tear line (see Figure J) and tear open (see Figure K).

Figure I

Figure J

Figure K

Step 4: Pour the entire contents of the HARVONI oral pellets packet directly in the mouth and swallow without chewing to avoid a bitter taste (see Figure L). Water may be taken after swallowing the pellets, if needed. Make sure that no HARVONI oral pellets remain in the packet. If your healthcare provider prescribed more than one HARVONI oral pellets packet, repeat Steps 1 through 4.

Figure L

Storing HARVONI oral pellets

- Store HARVONI pellets below 86°F (30°C).
  - Keep HARVONI oral pellets and all medicines out of the reach of children.

Disposing of HARVONI oral pellets

- Throw away any unused portion. Do not store and reuse any leftover HARVONI mixture (pellets mixed with food).

For more information, call 1-800-445-3235 or go to www.HARVONI.com.

Manufactured for and distributed by: Gilead Sciences, Inc., Foster City, CA 94404
HARVONI is a trademark of Gilead Sciences, Inc., or its related companies.

© 2024 Gilead Sciences, Inc. All rights reserved.
205834-GS-012

This Instructions for Use has been approved by the U.S. Food and Drug Administration.
Issued: March 2020

PRINCIPAL DISPLAY PANEL - 90 mg/400 mg Tablet Bottle Label

NDC 61958-1801-1
28 tablets

Harvoni®
(ledipasvir, sofosbuvir)
tablets, 90 mg/400 mg

Take 1 tablet once daily

Note to pharmacist:
Do not cover ALERT box with pharmacy label.

ALERT: Find out about medicines that
should NOT be taken with Harvoni

PRINCIPAL DISPLAY PANEL - 45 mg/200 mg Tablet Bottle Label

NDC 61958-1803-1
28 tablets

Harvoni®
(ledipasvir, sofosbuvir)
tablets

45 mg/200 mg

Note to pharmacist:
Do not cover ALERT box with pharmacy label.

ALERT: Find out about medicines that
should NOT be taken with Harvoni

PRINCIPAL DISPLAY PANEL - 33.75 mg/150 mg Pellet Packet Carton Label

NDC 61958-1805-1
28 packets

Harvoni®
(ledipasvir/sofosbuvir) oral pellets

33.75 mg/150 mg per packet

Rx only

Note to pharmacist: Do not cover ALERT box with pharmacy label.

ALERT: Find out about medicines that should NOT be taken with Harvoni

GILEAD

PRINCIPAL DISPLAY PANEL - 45 mg/200 mg Pellet Packet Carton Label

NDC 61958-1804-1
28 packets

Harvoni®
(ledipasvir/sofosbuvir) oral pellets

45 mg/200 mg per packet

Rx only

Note to pharmacist: Do not cover ALERT box with pharmacy label.

ALERT: Find out about medicines that should NOT be taken with Harvoni

GILEAD